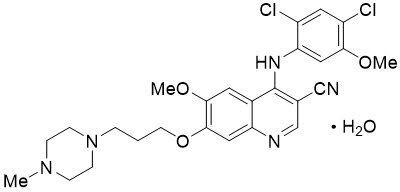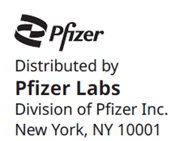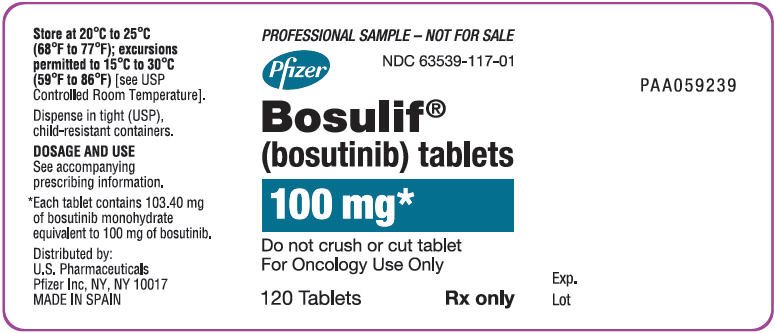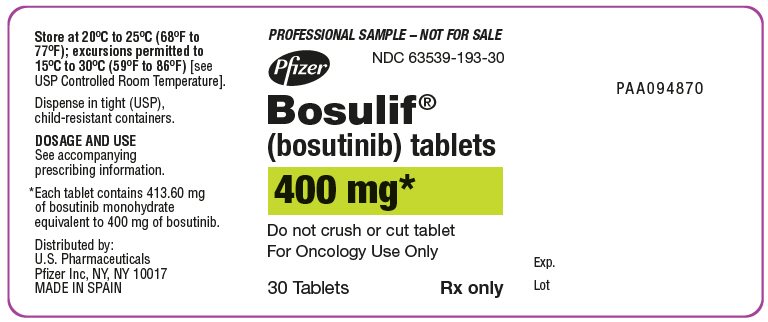 DRUG LABEL: BOSULIF
NDC: 63539-117 | Form: TABLET, FILM COATED
Manufacturer: U.S. Pharmaceuticals
Category: prescription | Type: HUMAN PRESCRIPTION DRUG LABEL
Date: 20241219

ACTIVE INGREDIENTS: BOSUTINIB MONOHYDRATE 100 mg/1 1
INACTIVE INGREDIENTS: MICROCRYSTALLINE CELLULOSE; CROSCARMELLOSE SODIUM; POVIDONE K25; MAGNESIUM STEARATE; POLYVINYL ALCOHOL, UNSPECIFIED; TITANIUM DIOXIDE; POLYETHYLENE GLYCOL 3350; TALC; FERRIC OXIDE YELLOW; POLOXAMER 188

HIGHLIGHTS OF PRESCRIBING INFORMATION

These highlights do not include all the information needed to use BOSULIF safely and effectively. See full prescribing information for BOSULIF.
BOSULIF® (bosutinib) tablets, for oral use
BOSULIF® (bosutinib) capsules, for oral use
Initial U.S. Approval: 2012

1 INDICATIONS AND USAGE

BOSULIF is a kinase inhibitor indicated for the treatment of

- adult and pediatric patients 1 year of age and older with chronic phase Ph+ chronic myelogenous leukemia (CML), newly-diagnosed or resistant or intolerant to prior therapy. (1)
- adult patients with accelerated, or blast phase Ph+ CML with resistance or intolerance to prior therapy. (1)

2 DOSAGE AND ADMINISTRATION

- Adult patients with newly-diagnosed chronic phase Ph+ CML: 400 mg orally once daily with food. (2.1)
- Adult patients with chronic, accelerated, or blast phase Ph+ CML with resistance or intolerance to prior therapy: 500 mg orally once daily with food. (2.1)
- Pediatric patients with newly-diagnosed chronic phase Ph+ CML: 300 mg/m^2 orally once daily with food. (2.1)
- Pediatric patients with chronic phase Ph+ CML with resistance or intolerance to prior therapy: 400 mg/m^2 orally once daily with food. (2.1)
- Consider dose escalation by increments of 100 mg once daily to a maximum of 600 mg daily in adult patients who do not reach complete hematologic, cytogenetic, or molecular response and do not have Grade 3 or greater adverse reactions. (2.2)
- Consider dose escalation by increments of 50 mg for those with a BSA <1.1 m^2 and 100 mg for those with a BSA ≥1.1 m^2 to a maximum of 600 mg daily in pediatric patients who do not reach sufficient response after 3 months. (2.2)
- Adjust dosage for toxicity and organ impairment (2)

3 DOSAGE FORMS AND STRENGTHS

- Tablets: 100 mg, 400 mg, and 500 mg. (3)
- Capsules 50 mg, 100 mg. (3)

4 CONTRAINDICATIONS

Hypersensitivity to BOSULIF. (4)

5 WARNINGS AND PRECAUTIONS

- Gastrointestinal Toxicity: Monitor and manage as necessary. Withhold, dose reduce, or discontinue BOSULIF. (2.3, 5.1)
- Myelosuppression: Monitor blood counts and manage as necessary. Withhold, dose reduce, or discontinue BOSULIF. (2.4, 5.2)
- Hepatic Toxicity: Monitor liver enzymes at least monthly for the first 3 months and as needed. Withhold, dose reduce, or discontinue BOSULIF. (2.3, 5.3)
- Cardiovascular Toxicity: Monitor and manage as necessary. Interrupt, dose reduce, or discontinue BOSULIF. (5.4)
- Fluid Retention: Monitor patients and manage using standard of care treatment. Interrupt, dose reduce, or discontinue BOSULIF. (2.3, 5.5)
- Renal Toxicity: Monitor patients for renal function at baseline and during therapy with BOSULIF. (5.6)
- Embryo-Fetal Toxicity: BOSULIF can cause fetal harm. Advise female patients of reproductive potential of potential risk to a fetus and to use effective contraception. (5.7)

6 ADVERSE REACTIONS

- Most common adverse reactions (≥20%), in adult and pediatric patients with CML are diarrhea, abdominal pain, vomiting, nausea, rash, fatigue, hepatic dysfunction, headache, pyrexia, decreased appetite respiratory tract infection, and constipation. The most common laboratory abnormalities (≥20%) in adult and pediatric patients are creatinine increased, hemoglobin decreased, lymphocyte count decreased, platelets decreased, ALT increased, calcium decreased, white blood cell count decreased, AST increased, absolute neutrophil count decreased, glucose increased, phosphorus decreased, urate increased, alkaline phosphatase increased, lipase increased, creatine kinase increased, and amylase increased. (6.1)

To report SUSPECTED ADVERSE REACTIONS, contact Pfizer Inc. at 1-800-438-1985 or FDA at 1-800-FDA-1088 or www.fda.gov/medwatch.

7 DRUG INTERACTIONS

- Strong and Moderate CYP3A Inhibitors: Avoid concomitant use with BOSULIF. (7.1)
- Strong CYP3A Inducers: Avoid concomitant use with BOSULIF. (7.1)
- Proton Pump Inhibitors: Use short-acting antacids or H2 blockers as an alternative to proton pump inhibitors. (7.1)

8 USE IN SPECIFIC POPULATIONS

Lactation: Advise women not to breastfeed. (8.2)

FULL PRESCRIBING INFORMATION

1 INDICATIONS AND USAGE

BOSULIF is indicated for the treatment of:

- Adult and pediatric patients 1 year of age and older with chronic phase (CP) Philadelphia chromosome-positive chronic myelogenous leukemia (Ph+ CML), newly-diagnosed or resistant or intolerant to prior therapy [see Clinical Studies (14.1, 14.2, 14.3)].
- Adult patients with accelerated phase (AP), or blast phase (BP) Ph+ CML with resistance or intolerance to prior therapy [see Clinical Studies (14.2)].

2 DOSAGE AND ADMINISTRATION

2.1 Recommended Dosage

The recommended dosage is taken orally once daily with food. Swallow tablets whole. Do not cut, crush, break or chew tablets. Continue treatment with BOSULIF until disease progression or intolerance to therapy.

Capsules may be swallowed whole. For patients who are unable to swallow a whole capsule(s), each capsule can be opened and the contents mixed with applesauce or yogurt. Mixing the capsule contents with applesauce or yogurt cannot be considered a substitute of a proper meal.

If a dose is missed beyond 12 hours, the patient should skip the dose and take the usual prescribed dose on the following day.

Dosage in Adult Patients with Newly-Diagnosed CP Ph+ CML

The recommended dosage of BOSULIF is 400 mg orally once daily with food.

Dosage in Adult Patients with CP, AP, or BP Ph+ CML with Resistance or Intolerance to Prior Therapy

The recommended dosage of BOSULIF is 500 mg orally once daily with food.

Dosage in Pediatric Patients with Newly-Diagnosed CP Ph+ CML or with CP Ph+ CML with Resistance or Intolerance to Prior Therapy

The recommended dose of BOSULIF for pediatric patients with newly-diagnosed CP Ph+ CML is 300 mg/m^2 orally once daily with food and the recommended dosage for pediatric patients with CP Ph+ CML that is resistant or intolerant to prior therapy is 400 mg/m^2 orally once daily with food and dose recommendations are provided in Table 1. As appropriate, the desired dose can be attained by combining different strengths of BOSULIF tablets or capsules.

Table 1: Dosing of BOSULIF for Pediatric Patients with Newly-Diagnosed CP Ph+ CML or with CP Ph+ CML with Resistance or Intolerance to Prior Therapy
BSA [BSA=Body Surface Area] | Newly-Diagnosed Recommended Dose; (Once Daily) | Resistant or Intolerant Recommended Dose; (Once Daily)
< 0.55 m^2 | 150 mg | 200 mg
0.55 to < 0.63 m^2 | 200 mg | 250 mg
0.63 to < 0.75 m^2 | 200 mg | 300 mg
0.75 to < 0.9 m^2 | 250 mg | 350 mg
0.9 to < 1.1 m^2 | 300 mg | 400 mg
≥ 1.1 m^2 | 400 mg [maximum starting dose (corresponding to maximum starting dose in adult indication)] | 500 mg

Preparation Instructions for BOSULIF Capsules Mixed with Applesauce or Yogurt

For patients who are unable to swallow capsules, the contents of the capsules can be mixed with applesauce or yogurt. Remove the required number of capsules from the container to prepare the dose as instructed and the amount of either room temperature applesauce or yogurt in a clean container. Carefully open each capsule, add the entire capsule content of each capsule into the applesauce or yogurt, then mix the entire dose into the applesauce or yogurt. Patients should immediately consume the full mixture in its entirety, without chewing. Do not store the mixture for later use. If the entire preparation is not swallowed do not take an additional dose. Wait until the next day to resume dosing.

Table 2: BOSULIF Dose Using Capsules and Soft Food Volumes
Dose | Volume of Applesauce or Yogurt
100 mg | 10 mL (2 teaspoons)
150 mg | 15 mL (3 teaspoons)
200 mg | 20 mL (4 teaspoons)
250 mg | 25 mL (5 teaspoons)
300 mg | 30 mL (6 teaspoons)
350 mg | 30 mL (6 teaspoons)
400 mg | 35 mL (7 teaspoons)
450 mg | 40 mL (8 teaspoons)
500 mg | 45 mL (9 teaspoons)
550 mg | 45 mL (9 teaspoons)
600 mg | 50 mL (10 teaspoons)

2.2 Dose Escalation

In clinical studies of adult patients with Ph+ CML, dose escalation by increments of 100 mg once daily to a maximum of 600 mg once daily was allowed in patients who did not achieve or maintain a hematologic, cytogenetic, or molecular response and who did not have Grade 3 or higher adverse reactions at the recommended starting dosage.

In pediatric patients with BSA <1.1 m^2 and an insufficient response after 3 months consider increasing dose by 50 mg increments up to maximum of 100 mg above starting dose. Dose increases for insufficient response in pediatric patients with BSA ≥1.1 m^2 can be conducted similarly to adult recommendations in 100 mg increments.

The maximum dose in pediatric and adult patients is 600 mg once daily.

2.3 Dosage Adjustments for Non-Hematologic Adverse Reactions

Elevated liver transaminases: If elevations in liver transaminases greater than 5×institutional upper limit of normal (ULN) occur, withhold BOSULIF until recovery to less than or equal to 2.5×ULN and resume at 400 mg once daily thereafter. If recovery takes longer than 4 weeks, discontinue BOSULIF. If transaminase elevations greater than or equal to 3×ULN occur concurrently with bilirubin elevations greater than 2×ULN and alkaline phosphatase less than 2×ULN (Hy's law case definition), discontinue BOSULIF [see Warnings and Precautions (5.3)].

Diarrhea: For National Cancer Institute Common Terminology Criteria for Adverse Events (NCI CTCAE) Grade 3–4 diarrhea (increase of greater than or equal to 7 stools/day over baseline/pretreatment), withhold BOSULIF until recovery to Grade less than or equal to 1. BOSULIF may be resumed at 400 mg once daily [see Warnings and Precautions (5.1)].

For other clinically significant, moderate or severe non-hematological toxicity, withhold BOSULIF until the toxicity has resolved, then consider resuming BOSULIF at a dose reduced by 100 mg taken once daily. If clinically appropriate, consider re-escalating the dose of BOSULIF to the starting dose taken once daily.

In pediatric patients, dose adjustments for non-hematologic toxicities can be conducted similarly to adults, however the dose reduction increments may differ. For pediatric patients with BSA <1.1 m^2, reduce dose by 50 mg initially followed by additional 50 mg increment if the adverse reaction (AR) persists. For pediatric patients with BSA ≥1.1 m^2 or greater, reduce dose similarly to adults.

2.4 Dosage Adjustments for Myelosuppression

Dose reductions for severe or persistent neutropenia and thrombocytopenia are described below (Table 3).

Table 3: Dose Adjustments for Neutropenia and Thrombocytopenia in Adult and Pediatric Patients
ANC [Absolute Neutrophil Count] less than 1000×10^6/L; or; Platelets less than 50,000×10^6/L | Withhold BOSULIF until ANC greater than or equal to1000×10^6/L and platelets greater than or equal to 50,000×10^6/L.; Resume treatment with BOSULIF at the same dose if recovery occurs within 2 weeks. If blood counts remain low for greater than 2 weeks, upon recovery, reduce dose by 100 mg and resume treatment, or by 50 mg in pediatric patients with BSA <1.1 m^2 and resume treatment.; If cytopenia recurs, reduce dose by an additional 100 mg upon recovery and resume treatment, or by an additional 50 mg in pediatric patients with BSA <1.1 m^2 and resume treatment.

2.5 Dosage Adjustments for Renal Impairment or Hepatic Impairment

The recommended starting doses for patients with renal and hepatic impairment are described in Table 4 below.

Table 4: Dose Adjustments for Renal and Hepatic Impairment in Adult Patients
 |  | Recommended Starting Dosage
 |  | Newly-diagnosed chronic phase Ph+ CML | Chronic, accelerated, or blast phase Ph+ CML with resistance or intolerance to prior therapy
Normal renal and hepatic function |  | 400 mg daily | 500 mg daily
Renal impairment
 | Creatinine clearance 30 to 50 mL/min | 300 mg daily | 400 mg daily
 | Creatinine clearance less than 30 mL/min | 200 mg daily | 300 mg daily
Hepatic impairment
 | Mild (Child-Pugh A), Moderate (Child-Pugh B) or Severe (Child-Pugh C) | 200 mg daily | 200 mg daily
[see Use in Specific Populations (8.6, 8.7) and Clinical Pharmacology (12.3)].

Table 5: Dosage Adjustments for Renal and Hepatic Impairment in Pediatric Patients
 | Newly-Diagnosed CP Ph+ CML Recommended Starting Dose (Once Daily) By Organ Function
Pediatric Patients by Separated BSA [BSA=Body Surface Area] Band | Normal renal and hepatic function | Renal Impairment: Creatinine clearance 30 to 50 mL/min | Renal Impairment: Creatinine clearance less than 30 mL/min | Hepatic Impairment: Mild (Child-Pugh A), Moderate (Child-Pugh B) or Severe (Child-Pugh C)
Pediatric < 0.55 m^2 | 150 mg | 100 mg | 100 mg | 100 mg
Pediatric 0.55 to < 0.63 m^2 | 200 mg | 150 mg | 100 mg | 100 mg
Pediatric 0.63 to < 0.75 m^2 | 200 mg | 150 mg | 100 mg | 100 mg
Pediatric 0.75 to < 0.9 m^2 | 250 mg | 200 mg | 150 mg | 100 mg
Pediatric 0.9 to < 1.1 m^2 | 300 mg | 200 mg | 200 mg | 150 mg
Pediatric ≥ 1.1 m^2 | 400 mg | 300 mg | 200 mg | 200 mg
 | CP Ph+ CML with Resistance or Intolerance to Prior Therapy Recommended Starting Dose (Once Daily) By Organ Function
Pediatric Patients by Separated BSA Band | Normal renal and hepatic function | Renal Impairment: Creatinine clearance 30 to 50 mL/min | Renal Impairment: Creatinine clearance less than 30 mL/min | Hepatic Impairment: Mild (Child-Pugh A), Moderate (Child-Pugh B) or Severe (Child-Pugh C)
Pediatric < 0.55 m^2 | 200 mg | 150 mg | 100 mg | 100 mg
Pediatric 0.55 to < 0.63 m^2 | 250 mg | 200 mg | 150 mg | 100 mg
Pediatric 0.63 to < 0.75 m^2 | 300 mg | 200 mg | 200 mg | 150 mg
Pediatric 0.75 to < 0.9 m^2 | 350 mg | 250 mg | 200 mg | 150 mg
Pediatric 0.9 to < 1.1 m^2 | 400 mg | 300 mg | 250 mg | 200 mg
Pediatric ≥ 1.1 m^2 | 500 mg | 400 mg | 300 mg | 200 mg
[see Use in Specific Populations (8.6, 8.7) and Clinical Pharmacology (12.3)].

3 DOSAGE FORMS AND STRENGTHS

Tablets:

- 100 mg: yellow, oval, biconvex, film-coated tablets debossed with "Pfizer" on one side and "100" on the other.
- 400 mg: orange, oval, biconvex, film-coated tablets debossed with "Pfizer" on one side and "400" on the other.
- 500 mg: red, oval, biconvex, film-coated tablets debossed with "Pfizer" on one side and "500" on the other.

Capsules:

- 50 mg: white body/orange cap with “BOS 50” printed on the body and “Pfizer” printed on the cap in black ink.
- 100 mg: white body/brownish-red cap with “BOS 100” printed on the body and “Pfizer” printed on the cap in black ink.

4 CONTRAINDICATIONS

BOSULIF is contraindicated in patients with a history of hypersensitivity to BOSULIF. Reactions have included anaphylaxis [see Adverse Reactions (6.1)].

5 WARNINGS AND PRECAUTIONS

5.1 Gastrointestinal Toxicity

Diarrhea, nausea, vomiting, and abdominal pain occur with BOSULIF treatment. Monitor and manage patients using standards of care, including antidiarrheals, antiemetics, and fluid replacement.

In the randomized clinical trial in adult patients with newly-diagnosed Ph+ CML, the median time to onset for diarrhea (all grades) was 4 days and the median duration per event was 3 days.

Among 546 adult patients in a single-arm study in patients with CML who were resistant or intolerant to prior therapy, the median time to onset for diarrhea (all grades) was 2 days and the median duration per event was 2 days. Among the patients who experienced diarrhea, the median number of episodes of diarrhea per patient during treatment with BOSULIF was 3 (range 1–268).

Among 49 pediatric patients with newly-diagnosed CP Ph+ CML or who had CP Ph+ CML that was resistant or intolerant to prior therapy, the median time to onset for diarrhea (all grades) was 2 days and the duration was 2 days. Among patients who experienced diarrhea, the median number of episodes of diarrhea per patient during treatment with BOSULIF was 2 (range 1 – 198).

To manage gastrointestinal toxicity, withhold, dose reduce, or discontinue BOSULIF as necessary [see Dosage and Administration (2.3) and Adverse Reactions (6)].

5.2 Myelosuppression

Thrombocytopenia, anemia and neutropenia occur with BOSULIF treatment. Perform complete blood counts weekly for the first month of therapy and then monthly thereafter, or as clinically indicated. To manage myelosuppression, withhold, dose reduce, or discontinue BOSULIF as necessary [see Dosage and Administration (2.4) and Adverse Reactions (6)].

5.3 Hepatic Toxicity

Bosutinib may cause elevations in serum transaminases (alanine aminotransferase [ALT], aspartate aminotransferase [AST]).

Two cases consistent with drug induced liver injury (defined as concurrent elevations in ALT or AST greater than or equal to 3×ULN with total bilirubin greater than 2×ULN and alkaline phosphatase less than 2×ULN) have occurred without alternative causes. This represented 2 out 1711 patients in BOSULIF clinical trials.

In the 268 adult patients from the safety population in the randomized clinical trial in patients with newly-diagnosed CML in the BOSULIF treatment group, the incidence of ALT elevation was 68.3% and increased AST was 56%. Of patients who experienced increased transaminases of any grade, 73% experienced their first increase within the first 3 months. The median time to onset of increased ALT and AST was 29 and 56 days, respectively, and the median duration was 19 and 15 days, respectively.

Among the 546 adult patients in a single-arm study in patients with CML who were resistant or intolerant to prior therapy, the incidence of increased ALT was 53.3% and AST elevation was 46.7%. Sixty percent of the patients experienced an increase in either ALT or AST. Most cases of transaminase elevations in this study occurred early in treatment; of patients who experienced increased transaminases of any grade, more than 81% experienced their first increase within the first 3 months. The median time to onset of increased ALT and AST was 22 and 29 days, respectively, and the median duration for each was 21 days.

Among 49 pediatric patients with newly‑diagnosed CP Ph+ CML or who had CP Ph+ CML that was resistant or intolerant to prior therapy, the incidence based on laboratory data that worsened from baseline of increased ALT was 59% and of increased AST 51%. Seventy-six percent of the patients experienced an increase in either ALT or AST. Most cases of increased transaminases occurred early in treatment; of patients who experienced increased transaminases of any grade, 84% of patients experienced their first increases within the first 3 months. The median time to onset for adverse reactions of increased ALT and AST was 22 and 15 days, respectively. The median duration for adverse reactions of Grade 3 or 4 increased ALT or AST was 26 and 12 days, respectively.

Perform hepatic enzyme tests monthly for the first 3 months of BOSULIF treatment and as clinically indicated. In patients with transaminase elevations, monitor liver enzymes more frequently. Withhold, dose reduce, or discontinue BOSULIF as necessary [see Dosage and Administration (2.3) and Adverse Reactions (6)].

5.4 Cardiovascular Toxicity

BOSULIF can cause cardiovascular toxicity including cardiac failure, left ventricular dysfunction, and cardiac ischemic events. Cardiac failure events occurred more frequently in previously treated patients than in patients with newly diagnosed CML and were more frequent in patients with advanced age or risk factors, including previous medical history of cardiac failure. Cardiac ischemic events occurred in both previously treated patients and in patients with newly diagnosed CML and were more common in patients with coronary artery disease risk factors, including history of diabetes, body mass index greater than 30, hypertension, and vascular disorders.

In a randomized study of adult patients with newly diagnosed CML, cardiac failure occurred in 1.9% of patients treated with BOSULIF compared to 0.8% of patients treated with imatinib. Cardiac ischemic events occurred in 4.9% of patients treated with BOSULIF compared to 0.8% of patients treated with imatinib.

In a single-arm study in adult patients with CML who were resistant or intolerant to prior therapy, cardiac failure was observed in 5.3% of patients and cardiac ischemic events were observed in 5.1% of patients treated with BOSULIF.

Among 49 pediatric patients with newly diagnosed CP Ph+ CML or who had CP Ph+ CML that was resistant or intolerant to prior therapy, 4 (8%) patients had Grade 1-2 cardiac events, including tachycardia (n=2), angina pectoris, right bundle branch block, and sinus tachycardia (n=1 each).

Monitor patients for signs and symptoms consistent with cardiac failure and cardiac ischemia and treat as clinically indicated. Interrupt, dose reduce, or discontinue BOSULIF as necessary [see Dosage and Administration (2.3) and Adverse Reactions (6)].

5.5 Fluid Retention

Fluid retention occurs with BOSULIF and may manifest as pericardial effusion, pleural effusion, pulmonary edema, and/or peripheral edema.

In the randomized clinical trial of 268 adult patients with newly-diagnosed CML in the bosutinib treatment group, 3 patients (1.1%) experienced severe fluid retention of Grade 3, 1 patient experienced Grade 3 pericardial effusion, and 2 patients experienced Grade 3 pleural effusion. Among 546 adult patients in a single-arm study in patients with Ph+ CML who were resistant or intolerant to prior therapy, Grade 3 or 4 fluid retention was reported in 30 patients (6%). Some patients experienced more than one fluid retention event. Specifically, 24 patients experienced Grade 3 or 4 pleural effusions, 9 patients experienced Grade 3 or Grade 4 pericardial effusions, and 6 patients experienced Grade 3 edema.

Among 49 pediatric patients with newly diagnosed CP Ph+ CML or who had CP Ph+ CML that was resistant or intolerant to prior therapy, Grade 1-2 pericardial effusion, peripheral edema, and face edema were reported in 1 patient each.

Monitor and manage patients using standards of care. Interrupt, dose reduce or discontinue BOSULIF as necessary [see Dosage and Administration (2.3) and Adverse Reactions (6)].

5.6 Renal Toxicity

An on-treatment decline in estimated glomerular filtration rate (eGFR) has occurred in patients treated with BOSULIF. Table 6 identifies the shift from baseline to lowest observed eGFR during BOSULIF therapy for patients in the pooled leukemia studies regardless of line of therapy. The median duration of therapy with BOSULIF was approximately 24 months (range, 0.03 to 155) for patients in these studies.

Table 6: Shift From Baseline to Lowest Observed eGFR Group During Treatment Safety Population in Clinical Studies (N=1372) [Among the 1372 patients, eGFR was missing in 7 patients at baseline or on-therapy. There were no patients with kidney failure at baseline.]
Baseline |  | Follow-Up
Renal Function Status | N | Normal n (%) | Mild n (%) | Mild to Moderate n (%) | Moderate to Severe n (%) | Severe n (%) | Kidney Failure n (%)
Normal | 527 | 115 (21.8) | 330 (62.6) | 50 (9.5) | 23 (4.4) | 3 (0.6) | 5 (0.9)
Mild | 672 | 10 (1.5) | 259 (38.5) | 271 (40.3) | 96 (14.3) | 26 (3.9) | 6 (0.9)
Mild to Moderate | 137 | 0 | 6 (4.4) | 40 (29.2) | 66 (48.2) | 24 (17.5) | 1 (0.7)
Moderate to Severe | 33 | 0 | 1 (3.0) | 1 (3.0) | 8 (24.2) | 19 (57.6) | 4 (12.1)
Severe | 1 | 0 | 0 | 0 | 0 | 0 | 1 (100)
Total | 1370 | 125 (9.1) | 596 (43.5) | 362 (26.4) | 193 (14.1) | 72 (5.2) | 17 (1.2)
Abbreviations: eGFR=estimated glomerular filtration rate; N/n=number of patients.
Notes: eGFR was calculated using Modification in Diet in Renal Disease method (MDRD).
Notes: Grading is based on Kidney Disease Improving Global Outcomes (KDIGO) Classification by eGFR: Normal: greater than or equal to 90, Mild: 60 to less than 90, Mild to Moderate: 45 to less than 60, Moderate to Severe: 30 to less than 45, Severe: 15 to less than 30, Kidney Failure: less than 15 ml/min/1.73 m^2.

Overall, 45% of the pediatric patients with newly diagnosed CP Ph+ CML or resistant or intolerant CP Ph+ CML who had normal eGFR at baseline shifted to a maximum of mild, and 40% pediatric patients who had mild eGFR at baseline shifted to a maximum of moderate during treatment.

Monitor renal function at baseline and during therapy with BOSULIF, with particular attention to those patients who have preexisting renal impairment or risk factors for renal dysfunction. Consider dose adjustment in patients with baseline and treatment emergent renal impairment [see Dosage and Administration (2.5)].

5.7 Embryo-Fetal Toxicity

Based on findings from animal studies and its mechanism of action, BOSULIF can cause fetal harm when administered to a pregnant woman. There are no available data in pregnant women to inform the drug-associated risk. In animal reproduction studies conducted in rats and rabbits, oral administration of bosutinib during organogenesis caused adverse developmental outcomes, including structural abnormalities, embryo-fetal mortality, and alterations to growth at maternal exposures (AUC) as low as 1.2 times the human exposure at the dose of 500 mg/day. Advise pregnant women of the potential risk to a fetus. Advise females of reproductive potential to use effective contraception during treatment and for 2 weeks after the last dose [see Use in Specific Populations (8.1, 8.3) and Clinical Pharmacology (12.1)].

6 ADVERSE REACTIONS

The following clinically significant adverse reactions are discussed in greater detail in other sections of the labeling:

- Gastrointestinal toxicity [see Warnings and Precautions (5.1)].
- Myelosuppression [see Warnings and Precautions (5.2)].
- Hepatic toxicity [see Warnings and Precautions (5.3)].
- Cardiovascular toxicity [see Warnings and Precautions (5.4)].
- Fluid retention [see Warnings and Precautions (5.5)].
- Renal toxicity [see Warnings and Precautions (5.6)].

6.1 Clinical Trials Experience

Because clinical trials are conducted under widely varying conditions, adverse reaction rates observed in the clinical trials of a drug cannot be directly compared to rates in the clinical trials of another drug and may not reflect the rates observed in practice.

The most common adverse reactions, in ≥20% of adults with newly diagnosed CP Ph+ CML or CP, AP, or BP Ph+ CML with resistance or intolerance to prior therapy (N=814) were diarrhea (80%), rash (44%), nausea (44%), abdominal pain (43%), vomiting (33%), fatigue (33%), hepatic dysfunction (33%), respiratory tract infection (25%), pyrexia (24%), and headache (21%).

The most common laboratory abnormalities that worsened from baseline in ≥20% of adults were creatinine increased (93%), hemoglobin decreased (90%), lymphocyte count decreased (72%), platelets decreased (69%), ALT increased (58%), calcium decreased (53%), white blood cell count decreased (52%), absolute neutrophils count decreased (50%), AST increased (50%), glucose increased (46%), phosphorus decreased (44%), urate increased (41%), alkaline phosphatase increased (40%), lipase increased (36%), creatine kinase increased (29%), and amylase increased (24%).

The most common adverse reactions, in ≥20% of pediatric patients (N=49) were diarrhea (82%), abdominal pain (73%), vomiting (55%), nausea (49%), rash (49%), fatigue (37%), hepatic dysfunction (37%), headache (35%), pyrexia (31%), decreased appetite (27%), and constipation (20%).

The most common laboratory abnormalities that worsened from baseline in ≥20% of pediatric patients were creatinine increased (92%), alanine aminotransferase increased (59%), white blood cell count decreased (53%), aspartate aminotransferase increased (51%), platelet count decreased (49%), glucose increased (41%), calcium decreased (31%), hemoglobin decreased (31%), neutrophil count decreased (31%), lymphocyte count decreased (29%), serum amylase increased (27%), and CPK increased (25%).

Adverse Reactions in Adult Patients With Newly-Diagnosed CP CML

The clinical trial randomized and treated 533 patients with newly-diagnosed CP CML to receive BOSULIF 400 mg daily or imatinib 400 mg daily as single agents (Newly-Diagnosed CP CML Study) [see Clinical Studies (14.1)]. The safety population (received at least 1 dose of BOSULIF) included:

- two hundred sixty-eight (268) patients with newly-diagnosed CP CML had a median duration of BOSULIF treatment of 55 months (range: 0.3 to 60 months) and a median dose intensity of 394 mg/day.

Serious adverse reactions occurred in 22% of patients with newly-diagnosed CP CML who received bosutinib. Serious adverse reactions reported in >2% of patients included hepatic dysfunction (4.1%), pneumonia (3.4%), coronary artery disease (3.4%), and gastroenteritis (2.2%). Fatal adverse reactions occurred in 3 patients (1.1%) due to coronary artery disease (0.4%), cardiac failure acute (0.4%), and renal failure (0.4%).

Permanent discontinuation of bosutinib due to an adverse reaction occurred in 20% of patients with newly-diagnosed CP CML who received bosutinib. Adverse reactions which resulted in permanent discontinuation in > 2% of patients included hepatic dysfunction (9%).

Dose modifications (dose interruption or reductions) of bosutinib due to an adverse reaction occurred in 68% of patients with newly-diagnosed CP CML. Adverse reactions which required dose interruptions or reductions in >5% of patients included hepatic dysfunction (27%), thrombocytopenia (16%), diarrhea (16%), lipase increased (10%), neutropenia (7%), abdominal pain (6%), rash (5%).

The most common adverse reactions, in >20% of bosutinib-treated patients with newly-diagnosed CML (N=268) were diarrhea (75%), hepatic dysfunction (45%), rash (40%), abdominal pain (39%), nausea (37%), fatigue (33%), respiratory tract infection (27%), headache (22%), and vomiting (21%).

The most common laboratory abnormalities that worsened from baseline in ≥20% of patients were creatinine increased (94%), hemoglobin decreased (89%), lymphocyte count decreased (84%), ALT increased (68%), platelet count decreased (68%), glucose increased (57%), AST increased (56%), calcium decreased (55%), phosphorus decreased (54%), lipase increased (53%), white blood cell count decreased (50%), absolute neutrophil count decreased (42%), alkaline phosphatase increased (41%), creatine kinase increased (36%), and amylase increased (32%).

Table 7 identifies adverse reactions greater than or equal to 10% for All Grades and Grades 3 or 4 (3/4) for the Phase 3 CP CML safety population.

Table 7: Adverse Reactions (10% or Greater) in Patients With Newly-Diagnosed CML in Bosutinib 400 mg Study [Based on a Minimum of 57 Months of Follow-up. Adverse drug reactions are based on all-causality treatment-emergent adverse events. The commonality stratification is based on 'All Grades' under Total column. 'Grade 3', 'Grade 4' columns indicate maximum toxicity.]
 |  | Bosutinib 400 mg Chronic Phase CML (N=268) |  | Imatinib 400 mg Chronic Phase CML (N=265)
System Organ Class | Preferred Term | All Grades % | Grade 3/4 % | All Grades % | Grade 3/4 %
Gastrointestinal disorders | Diarrhea | 75 | 9 | 40 | 1
 | Abdominal pain [Abdominal pain includes the following preferred terms: Abdominal discomfort, Abdominal pain, Abdominal pain lower, Abdominal pain upper, Abdominal tenderness, Dyspepsia, Epigastric discomfort, Gastrointestinal pain.] | 39 | 2 | 27 | 1
 | Nausea | 37 | 0 | 42 | 0
 | Vomiting | 21 | 1 | 20 | 0
 | Constipation | 13 | 0 | 6 | 0
Hepatobiliary disorders | Hepatic dysfunction [Hepatic dysfunction includes the preferred terms: Alanine aminotransferase increased, Aspartate aminotransferase, Aspartate aminotransferase increased, Bilirubin conjugated increased, Blood alkaline phosphatase increased, Blood bilirubin increased, Drug-induced liver injury, Gamma-glutamyltransferase increased, Hepatic enzyme increased, Hepatic steatosis, Hepatitis, Hepatitis toxic, Hepatocellular injury, Hepatotoxicity, Hyperbilirubinemia, Jaundice, Liver disorder, Liver function test increased, Ocular icterus, Transaminases increased.] | 45 | 27 | 15 | 4
Skin and subcutaneous tissue disorders | Rash [Rash includes the following preferred terms: Acne, Blister, Dermatitis, Dermatitis acneiform, Dermatitis bullous, Dermatitis exfoliative generalized, Drug reaction with eosinophilia and systemic symptoms, Dyshidrotic eczema, Eczema, Eczema asteatotic, Erythema, Erythema nodosum, Genital rash, Lichen planus, Perivascular dermatitis, Photosensitivity reaction, Psoriasis, Rash, Rash erythematous, Rash macular, Rash maculo-papular, Rash papular, Rash pruritic, Rash pustular, Rash vesicular, Seborrhoeic keratosis, Skin discoloration, Skin exfoliation, Skin hypopigmentation, Skin irritation, Skin lesion, Stasis dermatitis.] | 40 | 2 | 30 | 2
 | Pruritus | 11 | <1 | 4 | 0
General disorders and administration-site conditions | Fatigue [Fatigue includes the following preferred terms: Asthenia, Fatigue, Malaise.] | 33 | 1 | 30 | <1
 | Pyrexia | 17 | 1 | 11 | 0
 | Edema [Edema includes the following preferred terms: Eye edema, Eyelid edema, Face edema, Edema, Edema peripheral, Orbital edema, Periorbital edema, Periorbital swelling, Peripheral swelling, Swelling, Swelling face, Swelling of eyelid, Swollen tongue.] | 15 | 0 | 46 | 2
Infections and infestations | Respiratory tract infection [Respiratory tract infection includes the following preferred terms: Nasopharyngitis, Respiratory tract congestion, Respiratory tract infection, Respiratory tract infection viral, Upper respiratory tract infection.] | 27 | 1 | 25 | <1
Nervous system disorders | Headache | 22 | 1 | 15 | 1
Musculoskeletal and connective tissue disorders | Arthralgia | 18 | 1 | 18 | <1
 | Back pain | 12 | <1 | 9 | <1
Respiratory, thoracic, and mediastinal disorders | Cough | 11 | 0 | 10 | 0
 | Dyspnea | 11 | 1 | 6 | 1
Metabolism and nutrition disorders | Decreased appetite | 11 | <1 | 6 | 0
Vascular disorders | Hypertension [Hypertension* includes the preferred terms: Blood pressure systolic increased, Hypertension, Hypertensive crisis, Hypertensive heart disease, Retinopathy hypertensive.] | 10 | 5 | 11 | 5

In the randomized study in patients with newly-diagnosed CP CML, one patient in the group treated with BOSULIF experienced a Grade 3 QTcF prolongation (>500 msec). Patients with uncontrolled or significant cardiovascular disease including QT interval prolongation were excluded by protocol.

Table 8 identifies the clinically relevant or severe Grade 3/4 laboratory test abnormalities for the Phase 3 newly-diagnosed CML safety population.

Table 8: Select Laboratory Abnormalities (>20%) That Worsened From Baseline in Patients with Newly-Diagnosed CML in Bosutinib 400 mg Study [Based on a Minimum of 57 Months of Follow-up.]
 | Bosutinib N=268 % |  | Imatinib N=265 %
 | All Grade | Grade 3–4 | All Grade | Grade 3–4
Hematology Parameters
Platelet Count decreased | 68 | 14 | 60 | 6
Absolute Neutrophil Count decreased | 42 | 9 | 65 | 20
Hemoglobin decreased | 89 | 9 | 90 | 7
White Blood Cell Count decreased | 50 | 6 | 70 | 8
Lymphocyte Count decreased | 84 | 12 | 82 | 14
Biochemistry Parameters
SGPT/ALT increased | 68 | 26 | 28 | 3
SGOT/AST increased | 56 | 13 | 29 | 3.4
Lipase increased | 53 | 19 | 35 | 8
Phosphorus decreased | 54 | 9 | 69 | 21
Amylase increased | 32 | 3.4 | 18 | 2.3
Alkaline Phosphatase increased | 41 | 0 | 43 | 0.4
Calcium decreased | 55 | 1.5 | 57 | 1.1
Glucose increased | 57 | 3 | 65 | 3.4
Creatine Kinase increased | 36 | 3 | 65 | 5
Creatinine increased | 94 | 1.1 | 98 | 0.8
Abbreviations: ALT=alanine aminotransferase; AST=aspartate aminotransferase; CML=chronic myelogenous leukemia; SGPT=serum glutamic-pyruvic transaminase; SGOT=serum glutamic-oxaloacetic transaminase; N/n=number of patients; ULN=upper limit of normal.
Graded using CTCAE v 4.03

Adverse Reactions in Adult Patients With Imatinib-Resistant or -Intolerant Ph+ CP, AP, and BP CML

The single-arm clinical trial enrolled patients with Ph+ CP, AP, or BP CML and with resistance or intolerance to prior therapy [see Clinical Studies (14.2)]. The safety population (received at least 1 dose of BOSULIF) included 546 CML patients:

- two hundred eighty-four (284) patients with CP CML previously treated with imatinib only who had a median duration of BOSULIF treatment of 26 months (range: 0.2 to 155 months), and a median dose intensity of 437 mg/day.
- one hundred nineteen (119) patients with CP CML previously treated with both imatinib and at least 1 additional tyrosine kinase inhibitor (TKI) who had a median duration of BOSULIF treatment of 9 months (range: 0.2 to 148 months) and a median dose intensity of 427 mg/day.
- one hundred forty-three (143) patients with advanced phase (AdvP) CML including 79 patients with AP CML and 64 patients with BP CML. In the patients with AP CML and BP CML, the median duration of BOSULIF treatment was 10 months (range: 0.1 to 140 months) and 3 months (range: 0.03 to 71 months), respectively. The median dose intensity was 406 mg/day, and 456 mg/day, in the AP CML and BP CML cohorts, respectively.

Serious adverse reactions occurred in 30% of patients in the safety population of the single-arm trial in patients with CML (N=546) who were resistant or intolerant to prior therapy. Serious adverse reactions reported in >2% of patients included pneumonia (7%), pleural effusion (6%), pyrexia (3.7%), coronary artery disease (3.5%), dyspnea (2.6%), rash (2.2%), thrombocytopenia (2%), abdominal pain (2%), and diarrhea (2%).

Fatal adverse reactions occurred in 12 patients (2.2%) due to coronary artery disease (0.9%), pneumonia (0.4%), respiratory failure (0.4%), gastrointestinal hemorrhage (0.2%), acute kidney injury (0.2%), and acute pulmonary edema (0.2%).

Permanent discontinuation of bosutinib due to an adverse reaction occurred in 22% of patients with CML who were resistant or intolerant to prior therapy. Adverse reactions which resulted in permanent discontinuation in >2% of patients included thrombocytopenia (6%), hepatic dysfunction (3.3%), and neutropenia (2%).

Dose modifications (dose interruption or reductions) of bosutinib due to an adverse reaction occurred in 66% of patients with CML who were resistant or intolerant to prior therapy. Adverse reactions which required dose interruptions or reductions in >5% of patients included thrombocytopenia (24%), diarrhea (14%), rash (13%), hepatic dysfunction (10%), neutropenia (9%), pleural effusion (8%), vomiting (7%), anemia (6%), and abdominal pain (6%).

The most common adverse reactions, in ≥20% of patients in the safety population of the single-arm trial in patients with CML (N=546) who were resistant or intolerant to prior therapy were diarrhea (83%), nausea (47%), rash (46%), abdominal pain (45%), vomiting (39%), fatigue (33%), pyrexia (28%), hepatic dysfunction (27%), respiratory tract infection (24%), cough (23%), and headache (21%).

The most common laboratory abnormalities that worsened from baseline in ≥20% were creatinine increased (93%), hemoglobin decreased (91%), lymphocyte decreased (80%), platelets decreased (69%), absolute neutrophil count (54%), ALT increased (53%), calcium decreased (53%), white blood cell count decreased (52%), urate increased (48%), AST increased (47%), phosphorus decreased (39%), alkaline phosphatase increased (39%), lipase increased (28%), magnesium increased (25%), potassium decreased (24%), potassium increased (23%). See Table 10 for Grade 3/4 laboratory abnormalities.

Table 9 identifies adverse reactions greater than or equal to 10% for All Grades and Grades 3 or 4 for the Phase 1/2 CML safety population based on long-term follow-up.

Table 9: Adverse Reactions (10% or Greater) in Patients With CML Who Were Resistant or Intolerant to Prior Therapy in Single-Arm Trial [Based on a Minimum of 105 Months of Follow-up. Adverse drug reactions are based on all-causality treatment-emergent adverse events. The commonality stratification is based on 'All Grades' under Total column. 'Grade 3', 'Grade 4' columns indicate maximum toxicity]
 |  | CP CML (N=403) |  | AdvP CML (N=143)
System Organ Class | Preferred Term | All Grades % | Grade 3/4 % | All Grades % | Grade 3/4 %
Gastrointestinal disorders | Diarrhea | 85 | 10 | 76 | 4
 | Abdominal pain [Abdominal pain includes the following preferred terms: Abdominal discomfort, Abdominal pain, Abdominal pain lower, Abdominal pain upper, Abdominal tenderness, Dyspepsia, Epigastric discomfort, Gastrointestinal pain, Hepatic pain.] | 49 | 2 | 36 | 7
 | Nausea | 47 | 1 | 48 | 2
 | Vomiting | 38 | 3 | 43 | 3
 | Constipation | 15 | <1 | 17 | 1
Skin and subcutaneous tissue disorders | Rash [Rash includes the following preferred terms: Acarodermatitis, Acne, Angular cheilitis, Blister, Dermatitis, Dermatitis acneiform, Dermatitis psoriasiform, Drug eruption, Eczema, Eczema asteatotic, Erythema, Erythema annulare, Exfoliative rash, Lichenoid keratosis, Palmar erythema, Photosensitivity reaction, Pigmentation disorder, Psoriasis, Pyoderma gangrenosum, Pyogenic granuloma, Rash, Rash erythematous, Rash generalised, Rash macular, Rash maculo-papular, Rash pruritic, Rash pustular, Seborrhoeic dermatitis, Seborrhoeic keratosis, Skin depigmentation, Skin discoloration, Skin disorder, Skin exfoliation, Skin hyperpigmentation, Skin hypopigmentation, Skin irritation, Skin lesion, Skin plaque, Skin toxicity, Stasis dermatitis.] | 48 | 9 | 42 | 5
 | Pruritus | 12 | 1 | 7 | 0
General disorders and administration-site conditions | Fatigue | 35 | 3 | 27 | 6
 | Pyrexia | 25 | 1 | 37 | 3
 | Edema [Edema includes the following preferred terms: Eye edema, Eyelid edema, Face edema, Generalized edema, Localized edema, Edema, Edema peripheral, Penile edema, Periorbital edema, Periorbital swelling, Peripheral swelling, Scrotal edema, Scrotal swelling, Swelling, Swelling face, Swelling of eyelid, Testicular edema, Tongue edema.] | 19 | <1 | 17 | 1
 | Chest pain [Chest pain includes the following preferred terms: Chest discomfort, Chest pain.] | 8 | 1 | 12 | 1
Hepatobiliary disorders | Hepatic dysfunction [Hepatic dysfunction includes the following preferred terms: Alanine aminotransferase increased, Aspartate aminotransferase increased, Bilirubin conjugated increased, Blood alkaline phosphatase increased, Blood bilirubin increased, Blood bilirubin unconjugated increased, Gamma-glutamyltransferase increased, Hepatic enzyme increased, Hepatic function abnormal, Hepatic steatosis, Hepatitis toxic, Hepatomegaly, Hepatotoxicity, Hyperbilirubinemia, Liver disorder, Liver function test abnormal, Liver function test increased, Transaminases increased.] | 29 | 11 | 21 | 10
Infections and infestations | Respiratory tract infection [Respiratory tract infection includes the following preferred terms: Nasopharyngitis, Respiratory tract congestion, Respiratory tract infection, Respiratory tract infection viral, Upper respiratory tract infection, Viral upper respiratory tract infection.] | 27 | <1 | 17 | 0
 | Influenza [Influenza includes the following preferred terms: H1N1 influenza, Influenza.] | 11 | 1 | 3 | 0
 | Pneumonia [Pneumonia includes the following preferred terms: Atypical pneumonia, Lower respiratory tract congestion, Lower respiratory tract infection, Pneumonia, Pneumonia aspiration, Pneumonia bacterial, Pneumonia fungal, Pneumonia necrotising, Pneumonia streptococcal.] | 10 | 4 | 18 | 12
Respiratory, thoracic, and mediastinal disorders | Cough | 24 | 0 | 22 | 0
 | Pleural effusion | 14 | 4 | 9 | 4
 | Dyspnea | 12 | 2 | 20 | 6
Nervous system disorders | Headache | 21 | 1 | 18 | 4
 | Dizziness | 11 | 0 | 14 | 1
Musculoskeletal and connective tissue disorders | Arthralgia | 19 | 1 | 15 | 0
 | Back pain | 14 | 1 | 8 | 1
Metabolism and nutrition disorders | Decreased appetite | 14 | 1 | 14 | 0
Vascular disorders | Hypertension [Hypertension* includes the following preferred terms: Blood pressure increased, Blood pressure systolic increased, Essential hypertension, Hypertension, Hypertensive crisis, Retinopathy hypertensive. * ADR identified post-marketing] | 11 | 3 | 8 | 3
ADR Definition

In the single-arm study in patients with CML who were resistant or intolerant to prior therapy, 2 patients (0.4%) experienced QTcF interval of greater than 500 milliseconds. Patients with uncontrolled or significant cardiovascular disease including QT interval prolongation were excluded by protocol.

Table 10 identifies the clinically relevant or severe Grade 3/4 laboratory test abnormalities for the safety population of the study in patients with CML who were resistant or intolerant to prior therapy based on long-term follow-up.

Table 10: Number (%) of Patients With Clinically Relevant All Grade or Grade 3/4 Laboratory Test Abnormalities in the Safety Population of the Study of Patients With CML Who Were Resistant or Intolerant to Prior Therapy [Based on a Minimum of 105 Months of Follow-up.]
 | CP CML N=403 % |  | AdvP CML N=143 %
 | All grade | Grade 3/4 | All grade | Grade 3/4
Hematology Parameters
Platelet Count decreased | 66 | 26 | 80 | 57
Absolute Neutrophil Count decreased | 50 | 16 | 66 | 39
Hemoglobin decreased | 89 | 13 | 97 | 38
Lymphocyte decreased | 79 | 14 | 82 | 21
White Blood Cell Count decreased | 51 | 7 | 57 | 27
Biochemistry Parameters
SGPT/ALT increased | 58 | 11 | 39 | 6
SGOT/AST increased | 50 | 5 | 37 | 3.5
Lipase increased | 32 | 12 | 19 | 6
Phosphorus decreased | 41 | 8 | 33 | 7
Total Bilirubin increased | 16 | 0.7 | 22 | 2.8
Creatinine increased | 95 | 3 | 87 | 1.4
Alkaline Phosphatase increased | 39 | 0 | 39 | 1.4
Glucose increased | 42 | 2.7 | 39 | 6
Sodium increased | 23 | 0.5 | 11 | 0
Sodium decreased | 18 | 2.2 | 27 | 6
Calcium decreased | 55 | 4.7 | 45 | 3.5
Urate increased | 49 | 6 | 43 | 6
Magnesium increased | 27 | 7 | 18 | 4.9
Potassium decreased | 22 | 1.7 | 29 | 4.9
Potassium increased | 25 | 2.7 | 19 | 2.1
Abbreviations: AdvP=advanced phase; ALT=alanine aminotransferase; AST=aspartate aminotransferase; CML=chronic myelogenous leukemia; CP=chronic phase; N/n=number of patients; SGPT=serum glutamate-pyruvate transaminase; SGOT=serum glutamate-oxaloacetate aminotransferase; ULN=upper limit of normal.

Pediatric Patients with Newly-Diagnosed CP Ph+ CML or CP Ph+ CML that is Resistant or Intolerant to Prior Therapy

The safety of BOSULIF was evaluated in BCHILD, a single-arm trial for the treatment of pediatric patients aged 1 year and older with newly-diagnosed CP Ph+ CML or in patients with CP Ph+ CML who are resistant or intolerant to prior therapy [see Clinical Studies (14.3)]. Patients received BOSULIF (n = 49) 300 mg/m^2 to 400 mg/m^2 orally once daily until disease progression or unacceptable toxicity. The median time on treatment with BOSULIF was 12.2 months (range, 0.2 to 60.9 months). Among patients who received BOSULIF, 77.6% were exposed for 6 months or longer and 51% were exposed for one year or longer.

Permanent discontinuation of BOSULIF due to an adverse reaction occurred in 20% of patients. Adverse reactions which resulted in permanent discontinuation in 2 or more patients included ALT increased (6%), AST increased (4%), diarrhea (4%), fatigue (4%) and rash maculo-papular (4%).

The most common adverse reactions, in ≥20% of BOSULIF-treated pediatric patients were diarrhea, abdominal pain, vomiting, nausea, rash, fatigue, hepatic dysfunction, headache, pyrexia, decreased appetite, and constipation.

Table 11 summarizes the adverse reactions in BCHILD.

Table 11: Adverse Reactions (10% or Greater) in Pediatric Patients with Newly Diagnosed CP Ph+ CML or CP Ph+ CML Resistant or Intolerant to Prior Therapy Who Received BOSULIF in BCHILD
System Organ Class | Preferred Term | BOSULIF Total (N=49); %
System Organ Class | Preferred Term | All Grades | Grade 3/4
Gastrointestinal disorders | Diarrhea | 82 | 12
 | Abdominal pain [Abdominal pain includes the following preferred terms: Abdominal discomfort, Abdominal pain, Abdominal pain lower, Abdominal pain upper, Abdominal tenderness, Dyspepsia, Epigastric discomfort, Gastrointestinal pain, Hepatic pain.] | 73 | 4
 | Vomiting | 55 | 6
 | Nausea | 49 | 2
 | Constipation | 20 | 0
Skin and subcutaneous tissue disorders | Rash [Rash includes the following preferred terms: Acarodermatitis, Acne, Angular cheilitis, Blister, Dermatitis, Dermatitis acneiform, Dermatitis bullous, Dermatitis exfoliative generalized, Dermatitis psoriasiform, Drug eruption, Drug reaction with eosinophilia and systemic symptoms, Dyshidrotic eczema, Eczema, Eczema asteatotic, Erythema, Erythema annulare, Erythema nodosum, Exfoliative rash, Genital rash, Lichen planus, Lichenoid keratosis, Palmar erythema, Palmar-plantar erythrodysesthesia syndrome, Perivascular dermatitis, Photosensitivity reaction, Pigmentation disorder, Pruritus allergic, Psoriasis, Punctate keratitis, Pyoderma gangrenosum, Pyogenic granuloma, Rash, Rash erythematous, Rash generalized, Rash macular, Rash maculo-papular, Rash papular, Rash pruritic, Rash pustular, Rash vesicular, Seborrheic dermatitis, Seborrhoeic keratosis, Skin depigmentation, Skin discoloration, Skin disorder, Skin exfoliation, Skin hyperpigmentation, Skin hypopigmentation, Skin irritation, Skin lesion, Skin plaque, Skin reaction, Skin toxicity, Stasis dermatitis.] | 49 | 8
Hepatobiliary disorders | Hepatic dysfunction [Hepatic dysfunction includes the following preferred terms: Alanine aminotransferase abnormal, Alanine aminotransferase increased, Aspartate aminotransferase, Aspartate aminotransferase increased, Bilirubin conjugated increased, Blood alkaline phosphatase increased, Blood bilirubin increased, Blood bilirubin unconjugated increased, Gamma-glutamyltransferase increased, Hepatic enzyme increased, Hepatomegaly, Hepatosplenomegaly, Hyperbilirubinaemia, Jaundice, Liver function test abnormal, Liver function test increased, Ocular icterus, Transaminases increased, Hepatic function abnormal, Drug-induced liver injury, Hepatic steatosis, Hepatitis, Hepatitis toxic, Hepatobiliary disease, Hepatocellular injury, Hepatotoxicity, Liver disorder, Liver injury.] | 37 | 14
General disorders and administration-site conditions | Fatigue [Fatigue includes the following preferred terms: Asthenia, Fatigue, Malaise.] | 37 | 4
 | Pyrexia | 31 | 4
Nervous system disorders | Headache | 35 | 2
Metabolism and nutrition disorders | Decreased appetite | 27 | 2
Infections and infestations | Respiratory tract infection [Respiratory tract infection includes the following preferred terms: Nasopharyngitis, Respiratory tract congestion, Respiratory tract infection, Respiratory tract infection viral, Upper respiratory tract congestion, Upper respiratory tract infection, Upper respiratory tract inflammation, Viral upper respiratory tract infection.] | 12 | 2
Adverse drug reactions are based on all-causality treatment-emergent adverse reactions.
The commonality stratification is based on 'All Grades' under Bosutinib 400 mg column.
'Grade 3/4 columns indicate maximum toxicity.

The most common laboratory abnormalities that worsened from baseline in ≥20% of patients were creatinine increased, alanine aminotransferase increased, white blood cell count decreased, aspartate aminotransferase increased, platelet count decreased, glucose increased, calcium decreased, hemoglobin decreased, neutrophil count decreased, lymphocyte count decreased, serum amylase increased and CPK increased.

Table 12 summarizes laboratory test abnormalities in BCHILD.

Table 12: Laboratory Abnormalities (≥ 20%) That Worsened From Baseline in Pediatric Patients with Newly-Diagnosed CP Ph+ CML or CP Ph+ CML Resistant or Intolerant to Prior Therapy Who Received BOSULIF in BCHILD
 | BOSULIF (N= 49)
 | All Grade | Grade 3/4
 | % | %
Creatinine increased | 92 | 0
Alanine aminotransferase increased | 59 | 14
White blood cell count decreased | 53 | 4
Aspartate aminotransferase increased | 51 | 6
Platelet count decreased | 49 | 18
Glucose increased | 41 | 0
Calcium decreased | 31 | 0
Hemoglobin decreased | 31 | 8
Neutrophil count decreased | 31 | 12
Lymphocyte count decreased | 29 | 2
Serum amylase increased | 27 | 4
CPK increased | 25 | 0
Grades are defined using CTCAE V4.03. Based on CTCAE grading without regard to fasting status for 'Hyperglycemia' lab parameter.
Includes data up to 28 days after last dose of study treatment.

Additional Adverse Reactions From Multiple Clinical Trials

The following adverse reactions were reported in patients in clinical trials with BOSULIF (less than 10% of BOSULIF-treated patients). They represent an evaluation of the adverse reaction data from all 1372 patients with leukemia who received at least 1 dose of single-agent BOSULIF. These adverse reactions are presented by system organ class and are ranked by frequency. These adverse reactions are included based on clinical relevance and ranked in order of decreasing seriousness within each category.

Blood and Lymphatic System Disorders: 0.1% and less than 1% - Febrile neutropenia

Cardiac Disorders: 1% and less than 10% - Cardiac ischemia (includes Acute coronary syndrome, Acute myocardial infarction, Angina pectoris, Angina unstable, Arteriosclerosis coronary artery, Coronary artery disease, Coronary artery occlusion, Coronary artery stenosis, Myocardial infarction, Myocardial ischemia, Troponin increased), Pericardial effusion, Cardiac failure (includes Cardiac failure, Cardiac failure acute, Cardiac failure chronic, Cardiac failure congestive, Cardiogenic shock, Cardiorenal syndrome, Ejection fraction decreased, Left ventricular failure); 0.1% and less than 1% - Pericarditis

Ear and Labyrinth Disorders: 1% and less than 10% - Tinnitus

Endocrine Disorders: 1% and less than 10% - Hypothyroidism; 0.1% and less than 1% - Hyperthyroidism

Gastrointestinal Disorders: 1% and less than 10% - Gastritis, Pancreatitis (includes Edematous pancreatitis, Pancreatic enzymes increased, Pancreatitis, Pancreatitis acute, Pancreatitis chronic), Gastrointestinal hemorrhage (includes Anal hemorrhage, Gastric hemorrhage, Gastrointestinal hemorrhage, Intestinal hemorrhage, Lower gastrointestinal hemorrhage, Rectal hemorrhage, Upper gastrointestinal hemorrhage)

General Disorders and Administrative Site Conditions: 1% and less than 10% - Pain

Immune System Disorders: 1% and less than 10% - Drug hypersensitivity; 0.1% and less than 1% - Anaphylactic shock

Infections and Infestations: 1% and less than 10% - Bronchitis

Investigations: 1% and less than 10% - Electrocardiogram QT prolonged (includes Electrocardiogram QT prolonged, Long QT syndrome)

Metabolism and Nutrition Disorders: 1% and less than 10% - Dehydration

Musculoskeletal and Connective Tissue Disorders: 1% and less than 10% - Myalgia

Nervous System Disorders: 1% and less than 10% - Dysgeusia

Renal and Urinary Disorders: 1% and less than 10% - Acute kidney injury, Renal impairment, Renal failure

Respiratory, Thoracic and Mediastinal Disorders: 1% and less than 10% - Pulmonary hypertension (includes Pulmonary hypertension, Pulmonary arterial hypertension, Pulmonary arterial pressure increased); 0.1% and less than 1% - Acute pulmonary edema (includes Acute pulmonary edema, Pulmonary edema), Interstitial lung disease, Respiratory failure

Skin and Subcutaneous Disorders: 0.1% and less than 1% - Erythema multiforme

6.2 Postmarketing Experience

The following additional adverse reactions have been identified during post-approval use of BOSULIF. Because these reactions are reported voluntarily from a population of uncertain size, it is not always possible to reliably estimate their frequency or establish a causal relationship to drug exposure.

Blood and Lymphatic System Disorders: Thrombotic microangiopathy

Skin and Subcutaneous Tissue Disorders: Stevens-Johnson syndrome

7 DRUG INTERACTIONS

7.1 Effect of Other Drugs on BOSULIF

Strong or Moderate CYP3A Inhibitors

Avoid the concomitant use of strong or moderate CYP3A inhibitors with BOSULIF. Bosutinib is a CYP3A substrate. Concomitant use with a strong or moderate CYP3A inhibitor increases bosutinib Cmax and AUC [see Clinical Pharmacology (12.3)] which may increase the risk of toxicities.

Strong CYP3A Inducers

Avoid the concomitant use of strong CYP3A inducers with BOSULIF. Bosutinib is a CYP3A substrate. Concomitant use with a strong CYP3A inducer decreases bosutinib Cmax and AUC [see Clinical Pharmacology (12.3)] which may reduce BOSULIF efficacy.

Proton Pump Inhibitors (PPI)

As an alternative to PPIs, use short-acting antacids or H2 blockers and separate dosing by more than 2 hours from BOSULIF dosing. Bosutinib displays pH dependent aqueous solubility, Concomitant use with a PPI decreases bosutinib Cmax and AUC [see Clinical Pharmacology (12.3)] which may reduce BOSULIF efficacy.

8 USE IN SPECIFIC POPULATIONS

8.1 Pregnancy

Risk Summary

Based on findings from animal studies and its mechanism of action, BOSULIF can cause fetal harm when administered to a pregnant woman [see Clinical Pharmacology (12.1)].

There are no available data in pregnant women to inform the drug-associated risk. In animal reproduction studies conducted in rats and rabbits, oral administration of bosutinib during organogenesis caused adverse developmental outcomes, including structural abnormalities, embryo-fetal mortality, and alterations to growth at maternal exposures (AUC) as low as 1.2 times the human exposure at the dose of 500 mg/day (see Data). Advise pregnant women of the potential risk to a fetus.

The background risk of major birth defects and miscarriage for the indicated population is unknown. All pregnancies have a background risk of birth defect, loss, or other adverse outcomes. In the U.S. general population, the estimated background risk of major birth defects and miscarriage in clinically recognized pregnancies are 2–4% and 15–20%, respectively.

Data

Animal Data

In a rat fertility and early embryonic development study, bosutinib was administered orally to female rats for approximately 3 to 6 weeks, depending on day of mating (2 weeks prior to cohabitation with untreated breeder males until gestation day [GD] 7). Increased embryonic resorptions occurred at greater than or equal to 10 mg/kg/day of bosutinib (1.6 and 1.2 times the human exposure at the recommended doses of 400 or 500 mg/day, respectively), and decreased implantations and reduced number of viable embryos at 30 mg/kg/day of bosutinib (3.4 and 2.5 times the human exposure at the recommended doses of 400 or 500 mg/day, respectively).

In an embryo-fetal development study conducted in rabbits, bosutinib was administered orally to pregnant animals during the period of organogenesis at doses of 3, 10, and 30 mg/kg/day. At the maternally-toxic dose of 30 mg/kg/day of bosutinib, there were fetal anomalies (fused sternebrae, and 2 fetuses had various visceral observations), and an approximate 6% decrease in fetal body weight. The dose of 30 mg/kg/day resulted in exposures (AUC) approximately 5.1 and 3.8 times the human exposures at the recommended doses of 400 and 500 mg/day, respectively.

Fetal exposure to bosutinib-derived radioactivity during pregnancy was demonstrated in a placental-transfer study in pregnant rats. In a rat pre- and postnatal development study, bosutinib was administered orally to pregnant animals during the period of organogenesis through lactation day 20 at doses of 10, 30, and 70 mg/kg/day. Reduced number of pups born occurred at greater than or equal to 30 mg/kg/day bosutinib (3.4 and 2.5 times the human exposure at the recommended doses of 400 or 500 mg/day, respectively), and increased incidence of total litter loss and decreased growth of offspring after birth occurred at 70 mg/kg/day bosutinib (6.9 and 5.1 times the human exposure at the recommended doses of 400 or 500 mg/day, respectively).

8.2 Lactation

Risk Summary

No data are available regarding the presence of bosutinib or its metabolites in human milk or its effects on a breastfed child or on milk production. However, bosutinib is present in the milk of lactating rats. Because of the potential for serious adverse reactions in a nursing child, breastfeeding is not recommended during treatment with BOSULIF and for 2 weeks after the last dose.

Animal Data

After a single radiolabeled bosutinib dose to lactating rats, radioactivity was present in the plasma of suckling offspring for 24 to 48 hours.

8.3 Females and Males of Reproductive Potential

Based on findings from animal studies, BOSULIF can cause fetal harm when administered to a pregnant woman [see Use in Specific Populations (8.1)].

Pregnancy

Females of reproductive potential should have a pregnancy test prior to starting treatment with BOSULIF.

Contraception

Females

Advise females of reproductive potential to use effective contraception (methods that result in less than 1% pregnancy rates) during treatment with BOSULIF and for 2 weeks after the last dose.

Infertility

The risk of infertility in females or males of reproductive potential has not been studied in humans. Based on findings from animal studies, BOSULIF may cause reduced fertility in females and males of reproductive potential [see Nonclinical Toxicology (13.1)].

8.4 Pediatric Use

The safety and effectiveness of BOSULIF have been established in pediatric patients 1 year of age and older with newly-diagnosed CP Ph+ CML and CP Ph+ CML that is resistant or intolerant to prior therapy.

Use of BOSULIF for these indications is based on data from BCHILD [NCT04258943]. The study included pediatric patients with newly diagnosed CP Ph+ CML in the following age groups: 2 patients 1 year of age to less than 6 years of age, 3 patients 6 years of age to less than 12 years of age, and 10 patients 12 years of age to less than 17 years of age. The study also included pediatric patients with CP Ph+ CML that was resistant or intolerant to prior therapy in the following age groups: 4 patients 1 year of age to less than 6 years of age, 10 patients 6 years of age to less than 12 years of age, and 10 patients 12 years of age to less than 17 years of age [see Adverse Reactions (6.1) and Clinical Studies (14.3)]. BSA-normalized apparent clearance in 27 pediatric patients aged 4 to <17 years (141.3 L/h/m^2) was 29% higher than BSA-normalized apparent clearance in adult patients with CP Ph+ CML (109.2 L/h/m^2) [see Clinical Pharmacology (12.3)]. The recommended dosage of BOSULIF in pediatric patients is based on body surface area (BSA) [see Dosage and Administration (2.1)].

The safety and effectiveness of BOSULIF in pediatric patients younger than 1 year of age with newly diagnosed CP Ph+ CML, pediatric patients younger than 1 year of age with CP Ph+ CML that is resistant or intolerant to prior therapy, and pediatric patients with AP Ph+ CML or BP Ph+ CML have not been established.

8.5 Geriatric Use

In the single-arm study in patients with CML who were resistant or intolerant to prior therapy of BOSULIF in patients with Ph+ CML, 20% were age 65 and over, 4% were 75 and over. Of the 268 patients who received bosutinib in the study for newly diagnosed CML, 20% were age 65 and over, 5% were 75 and over. No overall differences in safety or effectiveness were observed between these patients and younger patients, and other reported clinical experience has not identified differences in responses between the elderly and younger patients, but greater sensitivity of some older individuals cannot be ruled out.

8.6 Renal Impairment

Reduce the BOSULIF starting dose in patients with moderate (creatinine clearance [CLcr] 30 to 50 mL/min, estimated by Cockcroft-Gault (C-G)) and severe (CLcr less than 30 mL/min, C-G) renal impairment at baseline. For patients who have declining renal function while on BOSULIF who cannot tolerate the starting dose, follow dose adjustment recommendations for toxicity [see Dosage and Administration (2.3, 2.5) and Clinical Pharmacology (12.3)]. BOSULIF has not been studied in patients undergoing hemodialysis.

8.7 Hepatic Impairment

Reduce the BOSULIF dosage in patients with hepatic impairment (Child-Pugh A, B, or C) [see Dosage and Administration (2.3, 2.5) and Clinical Pharmacology (12.3)].

10 OVERDOSAGE

Experience with BOSULIF overdose in clinical studies was limited to isolated cases. There were no reports of any serious adverse events associated with the overdoses. Patients who take an overdose of BOSULIF should be observed and given appropriate supportive treatment.

11 DESCRIPTION

BOSULIF contains bosutinib, a kinase inhibitor. Bosutinib is present as a monohydrate with a chemical name of 3-Quinolinecarbonitrile, 4-[(2,4-dichloro-5-methoxyphenyl)amino]-6-methoxy-7-[3-(4-methyl-1-piperazinyl) propoxy]-, hydrate (1:1). Its chemical formula is C26H29Cl2N5O3∙H2O (monohydrate); its molecular weight is 548.46 (monohydrate), equivalent to 530.46 (anhydrous). Bosutinib monohydrate has the following chemical structure:

Bosutinib monohydrate is a white to yellowish-tan powder. Bosutinib monohydrate has a pH dependent solubility across the physiological pH range. At or below pH 5, bosutinib monohydrate behaves as a highly soluble compound. Above pH 5, the solubility of bosutinib monohydrate reduces rapidly.

BOSULIF® (bosutinib) tablets are supplied for oral administration in 3 strengths: 100 mg, 400 mg and 500 mg. Each strength reflects the equivalent amount of bosutinib content (on anhydrous basis). The tablets contain the following inactive ingredients: croscarmellose sodium, iron oxide red (for 400 mg, and 500 mg tablet) and iron oxide yellow (for 100 mg, and 400 mg tablet), magnesium stearate, microcrystalline cellulose, poloxamer, polyethylene glycol, polyvinyl alcohol, povidone, talc and titanium dioxide.

BOSULIF® (bosutinib) capsules are supplied for oral administration in 2 strengths: 50 mg and 100 mg. Each strength reflects the equivalent amount of bosutinib (on anhydrous basis). The capsules contain the following inactive ingredients: croscarmellose sodium, gelatin, magnesium stearate, mannitol, microcrystalline cellulose, poloxamer, povidone, red iron oxide, titanium dioxide, yellow iron oxide. The printing ink contains black iron oxide, potassium hydroxide, propylene glycol, shellac, strong ammonia solution.

12 CLINICAL PHARMACOLOGY

12.1 Mechanism of Action

Bosutinib is a TKI. Bosutinib inhibits the BCR-ABL kinase that promotes CML; it is also an inhibitor of Src-family kinases including Src, Lyn, and Hck. Bosutinib inhibited 16 of 18 imatinib-resistant forms of BCR-ABL kinase expressed in murine myeloid cell lines. Bosutinib did not inhibit the T315I and V299L mutant cells.

12.2 Pharmacodynamics

A greater likelihood of response and a greater likelihood of safety events were observed with higher bosutinib exposure in clinical studies. The time course of bosutinib pharmacodynamic response has not been fully characterized.

Cardiac Electrophysiology

At a single oral dose of 500 mg BOSULIF with ketoconazole (a strong CYP3A inhibitor), BOSULIF does not prolong the QT interval to any clinically relevant extent.

12.3 Pharmacokinetics

Bosutinib pharmacokinetics were assessed following oral dosing with food in adult patients with CML and were presented as geometric mean (CV%), unless otherwise specified.

Bosutinib exhibits dose proportional increases in Cmax and AUC over the oral dose range of 200 to 800 mg (0.33 to 1.3 times the maximum approved recommended dosage of 600 mg). Bosutinib steady state Cmax was 127 ng/mL (31%), Ctrough was 68 ng/mL (39%) and AUC was 2370 ng•h/mL (34%) following multiple oral doses of BOSULIF 400 mg; Bosutinib steady state Cmax was 171 ng/mL (38%), Ctrough was 91 ng/mL (42%) and AUC was 3150 ng•h/mL (38%) following multiple oral doses of BOSULIF 500 mg. No clinically significant differences in the pharmacokinetics of bosutinib were observed following administration of either the tablet or capsule dosage forms of BOSULIF at the same dose, under fed conditions.

Absorption

The median bosutinib (minimum, maximum) time-‑to-Cmax (tmax) was 6.0 (6.0, 6.0) hours following oral administration of a single oral dose of BOSULIF 500 mg with food. The absolute bioavailability was 34% in healthy subjects.

Effect of Food

Bosutinib Cmax increased 1.8-fold and AUC increased 1.7-fold when BOSULIF tablets were given with a high fat meal to healthy subjects compared to administration under fasted condition. Bosutinib Cmax increased 1.6‑fold and AUC increased 1.5-fold when BOSULIF capsules were given with a high fat meal to healthy subjects compared to administration under fasted condition. The high-fat meal (800-1000 total calories) consisted of approximately 150 protein calories, 250 carbohydrate calories, and 500-600 fat calories.

No clinically significant differences in the pharmacokinetics of bosutinib were observed following administration of a BOSULIF capsule that was opened and the contents mixed with applesauce or yogurt immediately before use.

Distribution

The mean (SD) apparent bosutinib volume of distribution is 6080 (1230) L after an oral dose of 500 mg of BOSULIF.

Bosutinib protein binding is 94% in vitro and 96% ex vivo, and is independent of concentration.

Elimination

The mean (SD) bosutinib terminal phase elimination half life (t½) was 22.5 (1.7) hours, and the mean (SD) apparent clearance was 189 (48) L/h following a single oral dose of BOSULIF.

Metabolism

Bosutinib is primarily metabolized by CYP3A4.

Excretion

Following a single oral dose of [^14C] radiolabeled bosutinib without food, 91.3% of the dose was recovered in feces and 3.3% of the dose recovered in urine.

Specific Populations

Patients with Renal Impairment

Bosutinib AUC increased 1.4-fold in subjects with moderate renal impairment (CLcr: 30 to 50 mL/min, estimated by Cockcroft-Gault (C-G)) and increased 1.6-fold in subjects with severe renal impairment (CLcr less than 30 mL/min) following a single oral dose of BOSULIF 200 mg (0.33 times the maximum approved recommended dosage of 600 mg). No clinically significant difference in the pharmacokinetics of bosutinib was observed in subjects with mild renal impairment (CLcr: 51 to 80 mL/min, C-G). BOSULIF has not been studied in patients undergoing hemodialysis.

Patients with Hepatic Impairment

Bosutinib Cmax increased 2.4-fold, 2-fold, and 1.5-fold, and AUC increased 2.3-fold, 2-fold, and 1.9-fold in hepatic impairment Child-Pugh A, B, and C, respectively, following a single oral dose of BOSULIF 200 mg (0.33 times the maximum approved recommended dosage of 600 mg).

Pediatric Patients

The pharmacokinetics of bosutinib in 27 pediatric patients aged 4 to less than 17 years with newly diagnosed CP Ph+ CML or resistant/intolerant CP Ph+ CML were evaluated over the dose range of 300 mg/m^2 to 400 mg/m^2 administered orally once daily with food. Exposures increased in a dose proportional manner over the dose range of 300 mg/m^2 to 400 mg/m^2. The bosutinib median (min, max) tmax is approximately 3 hours post-dose (1, 8 hours). In 15 pediatric patients aged 4 to less than 17 years who received 300 mg/m^2 daily, steady state Cmax was 159 ng/mL (42%), Ctrough was 49 ng/mL (53%) and AUC was 2027 ng•h/mL (47%). In 6 pediatric patients aged 6 to less than 17 years who received 400 mg/m^2 daily, steady state Cmax was 198 ng/mL (37%), Ctrough was 42 ng/mL (105%), and AUC was 2514 ng•h/mL (35%).

An increase in BSA correlated with an increase in apparent clearance and exposure metrics did not significantly differ across BSA or age in pediatric patients following the approved recommended BSA-based dosage.

Drug Interaction Studies

Clinical Studies

Strong CYP3A Inhibitors: Bosutinib Cmax increased 5.2-fold and AUC increased 8.6-foldfollowing a single dose of BOSULIF 100 mg (0.17 times the maximum approved recommended dosage) without food when used concomitantly with 400 mg ketoconazole (a strong CYP3A inhibitor) administered over multiple daily doses.

Moderate CYP3A Inhibitors: Bosutinib Cmax increased 1.5-fold and AUC increased 2.0-fold following a single dose of BOSULIF 500 mg with food when administered concomitantly with 125 mg aprepitant (a moderate CYP3A inhibitor).

Strong CYP3A Inducers: Bosutinib Cmax decreased by 86% and AUC decreased by 94% following a single dose of BOSULIF 500 mg with food administered concomitantly with multiple daily doses of 600 mg of rifampin (a strong CYP3A inducer).

Proton Pump Inhibitors: Lansoprazole decreased bosutinib Cmax by 46% and AUC by 26% following a single oral dose of BOSULIF 400 mg without food when used concomitantly with lansoprazole 60 mg (proton pump inhibitor) administered over multiple daily doses. Bosutinib displays pH‑dependent aqueous solubility, in vitro [see Description (11)].

P-gp Substrates: No clinically significant differences in bosutinib pharmacokinetics were observed when used concomitantly with dabigatran etexilate mesylate (a P-glycoprotein (P-gp) substrate).

In Vitro Studies

Transporters Systems:

Bosutinib inhibits breast cancer resistance protein (BCRP)but, does not inhibit organic anion transporting polypeptide (OATP)1B1, OATP1B3, organic anion transporter (OAT)1, OAT3, organic cation transporter (OCT)1, and OCT2.

13 NONCLINICAL TOXICOLOGY

13.1 Carcinogenesis, Mutagenesis, Impairment of Fertility

Bosutinib was not carcinogenic in rats or transgenic mice. The rat 2-year carcinogenicity study was conducted at bosutinib oral doses up to 25 mg/kg in males and 15 mg/kg in females. Exposures at these doses were approximately 1.5 times (males) and 3.1 times (females) the human exposure at the 400 mg dose and 1.2 times (males) and 2.4 times (females) exposure in humans at the 500 mg dose. The 6-month RasH2 transgenic mouse carcinogenicity study was conducted at bosutinib oral doses up to 60 mg/kg.

Bosutinib was not mutagenic or clastogenic in a battery of tests, including the bacteria reverse mutation assay (Ames Test), the in vitro assay using human peripheral blood lymphocytes and the micronucleus test in orally treated male mice.

In a rat fertility study, drug-treated males were mated with untreated females, or untreated males were mated with drug-treated females. Females were administered the drug from pre-mating through early embryonic development. The dose of 70 mg/kg/day of bosutinib resulted in reduced fertility in males as demonstrated by 16% reduction in the number of pregnancies. There were no lesions in the male reproductive organs at this dose. This dose of 70 mg/kg/day resulted in exposure (AUC) in male rats approximately 1.5 times and equal to the human exposure at the recommended doses of 400 and 500 mg/day, respectively. Fertility (number of pregnancies) was not affected when female rats were treated with bosutinib. However, there were increased embryonic resorptions at greater than or equal to 10 mg/kg/day of bosutinib (1.6 and 1.2 times the human exposure at the recommended doses of 400 and 500 mg/day, respectively), and decreased implantations and reduced number of viable embryos at 30 mg/kg/day of bosutinib (3.4 and 2.5 times the human exposure at the recommended doses of 400 or 500 mg/day, respectively).

14 CLINICAL STUDIES

14.1 Adult Patients with Newly-Diagnosed CP Ph+ CML

The efficacy of BOSULIF in patients with newly-diagnosed chronic phase Ph+ CML was evaluated in the Bosutinib trial in First-line chrOnic myelogenous leukemia tREatment (BFORE) Trial: "A Multicenter Phase 3, Open-Label Study of Bosutinib Versus Imatinib in Adult Patients With Newly Diagnosed Chronic Phase Chronic Myelogenous Leukemia" [NCT02130557].

The BFORE Trial is a 2-arm, open-label, randomized, multicenter trial conducted to investigate the efficacy and safety of BOSULIF 400 mg once daily alone compared with imatinib 400 mg once daily alone in adult patients with newly-diagnosed CP Ph+ CML. The trial randomized 536 patients (268 in each arm) with Ph+ or Ph- newly-diagnosed CP CML (intent-to-treat [ITT] population) including 487 patients with Ph+ CML harboring b2a2 and/or b3a2 transcripts at baseline and baseline BCR-ABL copies >0 (modified intent-to-treat [mITT] population). Randomization was stratified by Sokal score and geographical region. All patients are being treated and/or followed for up to 5 years (240 weeks). Efficacy was evaluated in the mITT population. The major efficacy outcome measure was major molecular response (MMR) at 12 months (48 weeks) defined as ≤0.1% BCR-ABL ratio on international scale (corresponding to ≥3 log reduction from standardized baseline) with a minimum of 3000 ABL transcripts as assessed by the central laboratory. Additional efficacy outcomes included CCyR by 12 months, defined as the absence of Ph+ metaphases in chromosome banding analysis of ≥20 metaphases derived from bone marrow aspirate or MMR if an adequate cytogenetic assessment was unavailable and MMR by 18 months (72 weeks).

In the mITT population in this study, 57% of patients were males, 78% were Caucasian, and 19% were 65 years or older. The median age was 53 years. At baseline, the distribution of Sokal risk scores was similar in bosutinib and imatinib-treated patients (low risk: 35% and 39%; intermediate risk: 44% and 38%; high risk: 22% and 22%, respectively). After a minimum of 12 months follow-up, 78% of the 246 bosutinib-treated patients and 72% of the 239 imatinib-treated patients were still receiving treatment and with a minimum of 60 months of follow-up, 60% and 60% of patients, respectively, were still receiving treatment. The median treatment duration was 55.1 months for BOSULIF and 55.0 months for imatinib.

The efficacy results from the BFORE trial are summarized in Table 13.

Table 13: Summary of Major Molecular Response (MMR) and Complete Cytogenetic Response (CCyR), by Treatment Group in the Modified Intent-to-Treat (mITT) Population
Response | Bosutinib N=246 n (%) | Imatinib N=241 n (%) | 2-sided p-value
MMR at Month 12 (Week 48)
MMR (%) | 116 (47) | 89 (37) | 0.0200 [Derived from CMH test stratified by Geographical region and Sokal score at randomization.]
(95% CI) | (41, 53) | (31, 43)
CCyR by Month 12 (Week 48)
CCyR (%) | 190 (77) | 160 (66)
(95% CI) | (72, 83) | (60, 72) | 0.0075
MMR by Month 18 (Week 72)
MMR (%) | 150 (61) | 127 (53)
(95% CI) | (55, 67) | (46, 59) | 0.0606
Abbreviations: CCyR=complete cytogenetic response; CI=confidence interval; CMH=Cochran-Mantel-Haenszel; MMR=major molecular response; N/n=number of patients.

The MMR rate at Month 12 for all randomized patients (ITT population) was consistent with the mITT population (47% [95% CI: 41, 53] in the bosutinib treatment group and 36% [95% CI: 30, 42] in the imatinib treatment group; odds ratio of 1.57 [95% CI: 1.10, 2.22]). MMR by Month 60 (Week 240) in the mITT population was 74% (95% CI: 69, 80) in the bosutinib treatment group and 66% (95% CI: 60, 72) in the imatinib treatment group; odds ratio of 1.52 (95% CI: 1.02, 2.25). MMR by Month 60 in the ITT population was also consistent with the mITT population (1.57 [95% CI: 1.08, 2.28]).

After 60 months of follow-up, the median time to MMR in responders was 9.0 months for bosutinib and 11.9 months for imatinib.

By 60 months, the MMR rates in each Sokal risk group for the bosutinib and imatinib-treated patients, respectively, were 78% and 72% for low risk, 74% and 67% for intermediate risk and 68% and 52% for high risk.

After 60 months of follow-up, 6 (2%) bosutinib patients and 7 (3%) imatinib patients transformed to AP CML or BP CML while on treatment.

At 60 months, the estimated overall survival rate was 95% (95% CI: 91, 97) in the bosutinib group and 94% (95% CI: 90, 96) in the imatinib group.

14.2 Adult Patients with Imatinib-Resistant or -Intolerant Ph+ CP, AP, and BP CML

Study 200 (NCT00261846), a single-arm, open-label, multicenter study in patients with CML who were resistant or intolerant to prior therapy was conducted to evaluate the efficacy and safety of BOSULIF 500 mg once daily in patients with imatinib-resistant or -intolerant CML with separate cohorts for CP, AP, and BP disease previously treated with 1 prior TKI (imatinib) or more than 1 TKI (imatinib followed by dasatinib and/or nilotinib). The definition of imatinib resistance included (1) failure to achieve or maintain any hematologic improvement within 4 weeks; (2) failure to achieve a CHR by 3 months, cytogenetic response by 6 months or major cytogenetic response (MCyR) by 12 months; (3) progression of disease after a previous cytogenetic or hematologic response; or (4) presence of a genetic mutation in the BCR-ABL gene associated with imatinib resistance. Imatinib intolerance was defined as inability to tolerate imatinib due to toxicity, or progression on imatinib and inability to receive a higher dose due to toxicity. The definitions of resistance and intolerance to both dasatinib and nilotinib were similar to those for imatinib. The protocol was amended to exclude patients with a known history of the T315I mutation after 396 patients were enrolled in the trial.

The efficacy endpoints for patients with CP CML previously treated with 1 prior TKI (imatinib) were the rate of attaining MCyR by Week 24 and the duration of MCyR. The efficacy endpoints for patients with CP CML previously treated with both imatinib and at least 1 additional TKI were the cumulative rate of attaining MCyR by Week 24 and the duration of MCyR. The efficacy endpoints for patients with previously treated AP and BP CML were confirmed CHR and overall hematologic response (OHR).

The study enrolled 546 patients with CP, AP or BP CML. Of the total patient population 73% were imatinib resistant and 27% were imatinib intolerant. In this trial, 53% of patients were males, 65% were Caucasian, and 20% were 65 years old or older. Of the 546 treated patients, 506 were considered evaluable for cytogenetic or hematologic efficacy assessment. Patients were evaluable for efficacy if they had received at least 1 dose of BOSULIF and had a valid baseline efficacy assessment. Among evaluable patients, there were 262 patients with CP CML previously treated with 1 prior TKI (imatinib), 112 patients with CP CML previously treated with both imatinib and at least 1 additional TKI, and 132 patients with advanced phase CML previously treated with at least 1 TKI.

Median duration of BOSULIF treatment was 26 months in patients with CP CML previously treated with 1 TKI (imatinib), 9 months in patients with CP CML previously treated with imatinib and at least 1 additional TKI, 10 months in patients with AP CML previously treated with at least imatinib, and 3 months in patients with BP CML previously treated with at least imatinib.

The 24 week efficacy and MCyR at any time results are summarized in Table 14.

Table 14: Efficacy Results in Patients with Ph+ CP CML With Resistance to or Intolerance to Imatinib
 | Prior Treatment With Imatinib Only (N=262 evaluable) n (%) | Prior Treatment With Imatinib and Dasatinib or Nilotinib (N=112 evaluable) n (%)
By Week 24
MCyR | 105 (40.1) | 29 (25.9)
(95% CI) | (34.1, 46.3) | (18.1, 35.0)
MCyR any time | 156 (59.5) | 45 (40.2)
 | (53.3, 65.5) | (31.0, 49.9)
Abbreviations: CI=confidence interval; CML=chronic myelogenous leukemia; CP=chronic phase; MCyR=major cytogenetic response; N/n=number of patients; Ph+=Philadelphia chromosome positive.

The long-term follow-up data analysis was based on a minimum of 60 months for patients with CP CML treated with 1 prior TKI (imatinib) and a minimum of 48 months for patients with CP CML treated with imatinib and at least 1 additional TKI. For the 59.5% of patients with CP CML treated with 1 prior TKI (imatinib) who achieved a MCyR at any time, the median duration of MCyR was not reached. Among these patients, 65.4% and 42.9% had a MCyR lasting at least 18 and 54 months, respectively. For the 40.2% of patients with CP CML treated with imatinib and at least 1 additional TKI who achieved a MCyR at any time, the median duration of MCyR was not reached. Among these patients, 64.4% and 35.6% had a MCyR lasting at least 9 and 42 months, respectively. Of the 403 treated patients with CP CML, 20 patients had confirmed disease transformation to AP or BP while on treatment with BOSULIF.

The 48-week efficacy results in patients with accelerated and blast phases CML previously treated with at least imatinib are summarized in Table 15.

Table 15: Efficacy Results in Patients With Accelerated Phase and Blast Phase CML Previously Treated With at Least Imatinib
 | AP CML (N=72 evaluable) n (%) | BP CML (N=60 evaluable) n (%)
CHR [Overall hematologic response (OHR) = major hematologic response (complete hematologic response + no evidence of leukemia) or return to chronic phase (RCP). All responses were confirmed after 4 weeks. Complete hematologic response (CHR) for AP and BP CML: WBC less than or equal to institutional ULN, platelets greater than or equal to 100,000/mm^3 and less than 450,000/mm^3, absolute neutrophil count (ANC) greater than or equal to 1.0×10^9 /L, no blasts or promyelocytes in peripheral blood, less than 5% myelocytes + metamyelocytes in bone marrow, less than 20% basophils in peripheral blood, and no extramedullary involvement. No evidence of leukemia (NEL): Meets all other criteria for CHR except may have thrombocytopenia (platelets greater than or equal to 20,000/mm^3 and less than 100,000/mm^3) and/or neutropenia (ANC greater than or equal to 0.5×10^9 /L and less than 1.0×10^9 /L). Return to chronic phase (RCP) = disappearance of features defining accelerated or blast phases but still in chronic phase.] by Week 48 | 22 (30.6) | 10 (16.7)
(95% CI) | (20.2, 42.5) | (8.3, 28.5)
OHR by Week 48 | 41 (56.9) | 17 (28.3)
(95% CI) | (44.7, 68.6) | (17.5, 41.4)
Abbreviations: AP=accelerated phase; BP=blast phase; CHR=complete hematologic response; CI=confidence interval; CML=chronic myelogenous leukemia; CI=confidence interval, OHR=overall hematologic response, CHR=complete hematologic response, N/n=number of patients

The long-term follow-up data analysis was based on a minimum of 48 months for patients with AP CML and BP CML. Of the 79 treated patients with AP CML, 3 patients had confirmed disease transformation to BP while on BOSULIF treatment.

14.3 Pediatric Patients with Newly-Diagnosed CP Ph+ CML or with CP Ph+ CML with Resistance or Intolerance to Prior Therapy

The efficacy of BOSULIF in pediatric patients with newly-diagnosed (ND) chronic phase (CP) Ph+ CML and patients with resistant/intolerant (R/I) CP Ph+ CML was evaluated in the BCHILD trial [NCT04258943].

The BCHILD trial is a multicenter, non-randomized, open-label study conducted to identify a recommended dose of bosutinib administered orally once daily in pediatric patients with ND CP Ph+ CML and pediatric patients with R/I CP Ph+ CML who have received at least one prior TKI therapy, to estimate the safety and tolerability and efficacy, and to evaluate the PK of bosutinib in this patient population. The study enrolled 28 patients with R/I CP Ph+ CML treated with BOSULIF at 300 mg/m^2 to 400 mg/m^2 orally once daily, and 21 patients with ND CP Ph+ CML treated at 300 mg/m^2 orally once daily. Efficacy outcomes included CCyR (defined as the absence of Ph+ metaphases in chromosome banding analysis of ≥20 metaphases, or <1% BCR-ABL1–positive nuclei of at least 200 peripheral blood interphase nuclei analyzed by Fluorescence In Situ Hybridization (FISH), or MMR if an adequate cytogenetic assessment was unavailable), MCyR (defined as CCyR or partial cytogenetic response of 1% to 35% Ph+ metaphases), and MMR (defined as ≤0.1% BCR-ABL ratio on international scale [IS]) at any time on study.

Patients with ND CP Ph+ CML had a median age of 14 years (range 5 to 17 years); 68% were male; 81% were White, 14% were Black/African American, and 5% were race not reported.

The major (MCyR) and complete (CCyR) cytogenetic responses among patients with ND CP Ph+ CML were 76.2% (95% CI: 52.8, 91.8) and 71.4% (95% CI: 47.8, 88.7), respectively. The MMR among patients with ND CP Ph+ CML was 28.6% (95% CI: 11.3, 52.3). The median duration of follow-up was 14.2 months (range: 1.1, 26.3 months) in patients with ND CP CML.

Patients with R/I CP Ph+ CML included n=6 treated at 300 mg/m^2 (0.75 times the recommended dose), n=11 treated at 350 mg/m^2 (0.875 times the recommended dose), and n=11 at 400 mg/m^2. Overall (n=28), patients had a median age of 11.5 years (range: 1 to 17 years); 57% were male; 43% were White, 7% were Black/African American, 14% were Asian, and 36% were race not reported.

The major (MCyR) and complete (CCyR) cytogenetic responses among patients with R/I CP Ph+ CML were 82.1% (95% CI: 63.1, 93.9) and 78.6% (95% CI: 59.0, 91.7), respectively. The MMR among patients with R/I CP Ph+ CML was 50.0% (95% CI: 30.6, 69.4). The MR4.5 (defined as BCR-ABL/ABL IS ≤ 0.0032%) was 17.9% (95% CI: 6.1, 36.9). Among 14 patients who achieved MMR, two patients lost MMR after 13.6 months and 24.7 months on treatment. The median duration of follow-up for overall survival was 23.2 months (range: 1.0, 61.5 months) in patients with R/I CP Ph+ CML.

16 HOW SUPPLIED/STORAGE AND HANDLING

Tablets – How Supplied

BOSULIF (bosutinib) tablets are supplied for oral administration in 3 strengths: a 100 mg yellow, oval, biconvex, film-coated tablet debossed with "Pfizer" on one side and "100" on the other; a 400 mg orange, oval, biconvex, film coated tablet debossed with "Pfizer" on one side and "400" on the other; and a 500 mg red, oval, biconvex, film-coated tablet debossed with "Pfizer" on one side and "500" on the other. BOSULIF (bosutinib) tablets are available in the following packaging configurations with a child-resistant (CR) closure (Table 17). Bottles contain a desiccant.

Table 17: Tablet Presentations
BOSULIF Tablets
Package Configuration | Tablet Strength (mg) | NDC | Tablet Description
120 tablets per bottle | 100 mg | 0069-0135-01 | Yellow, oval, biconvex, film-coated tablets, debossed "Pfizer" on one side and "100" on the other.
30 tablets per bottle | 400 mg | 0069-0193-01 | Orange, oval, biconvex, film-coated tablet debossed with "Pfizer" on one side and "400" on the other.
30 tablets per bottle | 500 mg | 0069-0136-01 | Red, oval, biconvex, film-coated tablets, debossed "Pfizer" on one side and "500" on the other.
Abbreviation: NDC=National drug code.

Storage

Store at 20°C to 25°C (68°F to 77°F); excursions permitted to 15°C to 30°C (59°F to 86°F) [see USP Controlled Room Temperature].

Handling and Disposal

Procedures for proper disposal of anticancer drugs should be considered. Touching or handling crushed or broken tablets is to be avoided. Any unused product or waste material should be disposed of in accordance with local requirements, or drug take back programs.

Capsules - How Supplied

BOSULIF (bosutinib) capsules are supplied for oral administration in 2 strengths:

50 mg capsule: size 2 capsule, white body/orange cap with “BOS 50” printed on the body and “Pfizer” printed on the cap in black ink. 100 mg capsule: size 0 capsule, white body/brownish-red cap with “BOS 100” printed on the body and “Pfizer” printed on the cap in black ink. BOSULIF (bosutinib) capsules are available in the following packaging configurations with a CR closure (Table 18).

Table 18: Capsule Presentations
BOSULIF Capsules
Package Configuration Count | Capsule Strength (mg) | NDC | Capsule Description
30 capsules per bottle | 50 | 0069-0504-30 | Size 2 capsule, white body/orange cap with “BOS 50” printed on the body and “Pfizer” printed on the cap in black ink.
150 capsules per bottle | 100 | 0069-1014-15 | Size 0 capsule, white body/brownish-red cap with “BOS 100” printed on the body and “Pfizer” printed on the cap in black ink.
Abbreviation: NDC=National drug code.

Storage

Store at 20°C to 25°C (68°F to 77°F); excursions permitted to 15°C to 30°C (59°F to 86°F) [see USP Controlled Room Temperature] and Store and Dispense in Original Container.

Handling and Disposal

Procedures for proper disposal of anticancer drugs should be considered. Patients and/or caregivers must wear gloves while handling the drug product, and wash their hands once finished. Any unused product or waste material should be disposed of in accordance with local requirements.

17 PATIENT COUNSELING INFORMATION

Advise the patient to read the FDA-approved patient labeling (Patient Information and Instructions for Use).

- Dosage and Administration

Instruct patients to take BOSULIF exactly as prescribed, not to change their dose or to stop taking BOSULIF unless they are told to do so by their doctor. If patients miss a dose beyond 12 hours, they should be advised to take the next scheduled dose at its regular time. A double dose should not be taken to make up for any missed dose. Advise patients to take BOSULIF with food. Patients should be advised: “Swallow tablets whole. Do not crush, break, or cut tablet. Do not touch or handle crushed or broken tablets.” Patients should be advised: “Capsules may be swallowed whole. For those that cannot swallow the capsule whole, the capsule can be opened and the contents mixed with applesauce or yogurt.”

- Gastrointestinal Toxicity

Advise patients that they may experience diarrhea, nausea, vomiting, abdominal pain, or blood in their stools with BOSULIF and to seek medical attention promptly for these symptoms [see Warnings and Precautions (5.1)].

- Myelosuppression

Advise patients of the possibility of developing low blood cell counts and to immediately report fever, any suggestion of infection, or signs or symptoms suggestive of bleeding or easy bruising [see Warnings and Precautions (5.2)].

- Hepatic Toxicity

Advise patients of the possibility of developing liver function abnormalities and to immediately report jaundice [see Warnings and Precautions (5.3)].

- Cardiovascular Toxicity

Advise patients that cardiac failure, left ventricular dysfunction, and cardiac ischemic events have been reported. Advise patients to seek immediate medical attention if any symptoms suggestive of cardiac failure and cardiac ischemia occur, such as shortness of breath, weight gain, or fluid retention [see Warnings and Precautions (5.4)].

- Fluid Retention

Advise patients of the possibility of developing fluid retention (swelling, weight gain, or shortness of breath) and to seek medical attention promptly if these symptoms arise [see Warnings and Precautions (5.5)].

- Renal Toxicity

Advise patients of the possibility of developing renal problems and to immediately report frequent urination, polyuria or oliguria [see Warnings and Precautions (5.6)].

- Adverse Reactions

Advise patients that they may experience other adverse reactions such as respiratory tract infections, rash, fatigue, loss of appetite, headache, dizziness, back pain, arthralgia, pruritus or constipation with BOSULIF and to seek medical attention if symptoms are significant. There is a possibility of anaphylactic shock [see Contraindications (4) and Adverse Reactions (6)].

- Embryo-Fetal Toxicity

Advise females to inform their healthcare provider if they are pregnant or become pregnant. Advise female patients of the risk to a fetus and potential loss of the pregnancy [see Use in Specific Populations (8.1)].

Advise females of reproductive potential, to use effective contraception during treatment and for 2 weeks after receiving the last dose of BOSULIF [see Warnings and Precautions (5.7) and Use in Specific Populations (8.1, 8.3)].

Advise lactating women not to breastfeed during treatment with BOSULIF and for 2 weeks after the last dose [see Use in Specific Populations (8.2)].

- Drug Interactions

Advise patients that BOSULIF and certain other medicines, including over the counter medications or herbal supplements (such as St. John's wort) can interact with each other and may alter the effects of BOSULIF [see Drug Interactions (7)].

LAB-0443-19.0

PATIENT INFORMATION

BOSULIF® (BAH-su-lif)

(bosutinib)

tablets

BOSULIF® (BAH-su-lif)

(bosutinib)

capsules

What is BOSULIF?
BOSULIF is a prescription medicine used to treat:

- adults and children 1 year of age and older who have a certain type of leukemia called chronic phase (CP) Philadelphia chromosome-positive chronic myelogenous leukemia (Ph+ CML) who are newly-diagnosed or who no longer benefit from or did not tolerate other treatment.
- adults with accelerated phase (AP), or blast phase (BP) Ph+ CML who can no longer benefit from or did not tolerate other treatment.

It is not known if BOSULIF is safe and effective in children less than 1 year of age with CP Ph+ CML who are newly‑diagnosed or who no longer benefit from or did not tolerate other treatment or in children with AP Ph+ CML or BP Ph+ CML.

Do not take BOSULIF if you are allergic to bosutinib or any of the ingredients in BOSULIF. See the end of this leaflet for a complete list of ingredients of BOSULIF.

Before taking BOSULIF, tell your doctor about all of your medical conditions, including if you:

- have liver problems
- have heart problems
- have kidney problems
- have high blood pressure
- have diabetes
- are pregnant or plan to become pregnant. BOSULIF can harm your unborn baby. Females who are able to become pregnant should have a pregnancy test before starting treatment with BOSULIF. Tell your doctor right away if you become pregnant during treatment with BOSULIF.
  - Females who are able to become pregnant should use effective birth control (contraception) during treatment with BOSULIF and for 2 weeks after the last dose. Talk to your doctor about birth control methods that may be right for you.
- are breastfeeding or plan to breastfeed. It is not known if BOSULIF passes into your breast milk or if it can harm your baby. Do not breastfeed during treatment with BOSULIF and for 2 weeks after the last dose.

Tell your doctor about all the medicines you take, including prescription medicines, over-the-counter medicines, vitamins, and herbal supplements. When taken together, BOSULIF and certain other medicines can affect each other.
Know the medicines you take. Keep a list of your medicines and show it to your doctor and pharmacist when you get a new medicine.

How should I take BOSULIF?

- Take BOSULIF exactly as prescribed by your doctor.
- Do not change your dose or stop taking BOSULIF without first talking with your doctor.
- If your child takes BOSULIF, your healthcare provider will change the dose as your child grows.
- Take BOSULIF with food.
- Swallow BOSULIF tablets whole. Do not crush, break, chew or cut BOSULIF tablets. Do not touch or handle crushed or broken BOSULIF tablets.
- Swallow BOSULIF capsules whole. If you cannot swallow BOSULIF capsules whole, tell your healthcare provider.
- If you cannot swallow BOSULIF capsules whole, see the “Instructions for Use” for detailed instructions on how to prepare and give a dose of BOSULIF capsules by opening the capsules and mixing the capsule contents with applesauce or yogurt.
- If you take an antacid or H2 blocker medicine, take it at least 2 hours before or 2 hours after BOSULIF. If you take a Proton Pump Inhibitor (PPI) medicine, talk to your doctor or pharmacist.
- You should avoid grapefruit, grapefruit juice, and supplements that contain grapefruit extract during treatment with BOSULIF. Grapefruit products increase the amount of BOSULIF in your body.
- If you miss a dose of BOSULIF, take it as soon as you remember. If you miss a dose by more than 12 hours, skip that dose and take your next dose at your regular time. Do not take 2 doses at the same time.
- If you take too much BOSULIF, call your doctor or go to the nearest hospital emergency room right away.

What are the possible side effects of BOSULIF?
BOSULIF may cause serious side effects, including:

- Stomach problems. BOSULIF may cause stomach (abdomen) pain, nausea, diarrhea, vomiting, or blood in your stools. Get medical help right away for any stomach problems.
- Low blood cell counts. BOSULIF may cause low platelet counts (thrombocytopenia), low red blood cell counts (anemia) and low white blood cell counts (neutropenia). Your doctor should do blood tests to check your blood cell counts regularly during your treatment with BOSULIF. Call your doctor right away if you have unexpected bleeding or bruising, blood in your urine or stools, fever, or any signs of an infection.
- Liver problems. Your doctor should do blood tests to check your liver function regularly during your treatment with BOSULIF. Call your doctor right away if your skin or the white part of your eyes turns yellow (jaundice) or you have dark "tea color" urine.
- Heart problems. BOSULIF may cause heart problems, including heart failure and decreased blood flow to the heart which can lead to heart attack. Get medical help right away if you get shortness of breath, weight gain, chest pain, or swelling in your hands, ankles or feet.
- Your body may hold too much fluid (fluid retention). Fluid may build up in the lining of your lungs, the sac around your heart, or your stomach cavity. Get medical help right away if you get any of the following symptoms during your treatment with BOSULIF:

- shortness of breath and cough
- chest pain
- swelling in your hands, ankles, or feet

- swelling all over your body
- weight gain

- Kidney problems. Your doctor should do tests to check your kidney function when you start treatment with BOSULIF and during your treatment. Call your doctor right away if you get any of the following symptoms during your treatment with BOSULIF:
  - you urinate more often than normal
  - you urinate less often than normal
  - you make a much larger amount of urine than normal
  - you make a much smaller amount of urine than normal

The most common side effects of BOSULIF in adults and children with CML include:

- diarrhea
- stomach (abdominal) pain
- vomiting
- nausea
- rash
- tiredness
- liver problems

- headache
- fever
- decreased appetite
- respiratory tract infections (infections in nose, throat or lungs)
- constipation
- changes in certain blood tests. Your doctor may do blood tests during treatment with BOSULIF to check for changes

Tell your doctor or get medical help right away if you get respiratory tract infections, loss of appetite, headache, dizziness, back pain, joint pain, rash or itching while taking BOSULIF. These may be symptoms of a severe allergic reaction.
Your doctor may change your dose, temporarily stop, or permanently stop treatment with BOSULIF if you have certain side effects.
BOSULIF may cause fertility problems in females and males. This may affect your ability to have a child. Talk to your doctor if this is a concern for you.
Tell your doctor if you have any side effect that bothers you or that does not go away.
These are not all of the possible side effects of BOSULIF.
Call your doctor for medical advice about side effects. You may report side effects to FDA at 1-800-FDA-1088.

How should I store BOSULIF?

- Store BOSULIF tablets and capsules at room temperature between 68°F to 77°F (20°C to 25°C).
- The BOSULIF tablets and capsules bottle has a child-resistant closure.
- The BOSULIF tablets bottle contains a desiccant to help keep your medicine dry (protect it from moisture). Keep the desiccant in the bottle. Do not eat the desiccant.
- Store the BOSULIF capsules in the original bottle.
- Ask your doctor or pharmacist about the right way to throw away outdated or unused BOSULIF.

Keep BOSULIF and all medicines out of the reach of children.

General information about the safe and effective use of BOSULIF.
Medicines are sometimes prescribed for purposes other than those listed in a Patient Information leaflet. Do not use BOSULIF for a condition for which it is not prescribed. Do not give BOSULIF to other people even if they have the same symptoms you have. It may harm them. You can ask your doctor or pharmacist for information about BOSULIF that is written for health professionals.

What are the ingredients in BOSULIF?
Active ingredient: bosutinib.
Inactive ingredients: Tablets: croscarmellose sodium, iron oxide red (for 400 mg, and 500 mg tablet) and iron oxide yellow (for 100 mg, and 400 mg tablet), magnesium stearate, microcrystalline cellulose, poloxamer, polyethylene glycol, polyvinyl alcohol, povidone, talc and titanium dioxide. Capsules: croscarmellose sodium, gelatin, magnesium stearate, mannitol, microcrystalline cellulose, poloxamer, povidone, red iron oxide, titanium dioxide, yellow iron oxide. The printing ink contains black iron oxide, potassium hydroxide, propylene glycol, shellac, strong ammonia solution.

For more information, go to www.Bosulif.com or www.pfizermedicalinformation.com or call 1-800-438-1985.

This Patient Information has been approved by the U.S. Food and Drug Administration. Revised 12/2024

INSTRUCTIONS FOR USE

BOSULIF® (BAH-su-lif)

(bosutinib)

capsules

This Instructions for Use contains information on how to prepare and give a dose of BOSULIF capsules by opening the capsules and mixing the contents with applesauce or yogurt for people who cannot swallow capsules whole. Read this Instructions for Use before you prepare or give the first dose of BOSULIF, and each time you get a refill. Ask your healthcare provider or pharmacist if you have any questions.

Important information you need to know before preparing a dose of BOSULIF capsules:

- BOSULIF capsules can be opened and the capsules contents mixed with room temperature applesauce or yogurt.
- Only use applesauce or yogurt. Do not mix BOSULIF with other foods.
- Swallow all of the mixture right away, without chewing. Do not store the mixture for later use.
- If you do not swallow the entire BOSULIF mixture, do not mix another dose. Wait until the next day to take your regularly scheduled dose.
- Take the BOSULIF mixture with a full meal.

Preparing a dose of BOSULIF capsules:

Gather the following supplies:

- BOSULIF capsules
- small, clean container
- yogurt or applesauce
- teaspoon for mixing
- disposable gloves

Giving a dose of BOSULIF capsules:

Step 1: Choose a clean, flat work surface. Place all supplies on the work surface.

Step 2: Wash and dry your hands well.

Step 3: Put on disposable gloves

Step 4: Get the prescribed number of BOSULIF capsule(s) needed to prepare the dose.

Step 5: Add the amount of applesauce or yogurt needed for the prescribed dose to the container.

Dose | Amount of Applesauce or Yogurt
100 mg | 10 mL (2 teaspoons)
150 mg | 15 mL (3 teaspoons)
200 mg | 20 mL (4 teaspoons)
250 mg | 25 mL (5 teaspoons)
300 mg | 30 mL (6 teaspoons)
350 mg | 30 mL (6 teaspoons)
400 mg | 35 mL (7 teaspoons)
450 mg | 40 mL (8 teaspoons)
500 mg | 45 mL (9 teaspoons)
550 mg | 45 mL (9 teaspoons)
600 mg | 50 mL (10 teaspoons)

Step 6: Carefully open each of the BOSULIF capsule(s) needed for the dose and empty the entire contents into the applesauce or yogurt. Mix the entire capsule contents with the applesauce or yogurt in the container.

Step 7: Swallow all of the mixture right away, without chewing.

Step 8: Dispose of (throw away) the empty BOSULIF capsule shell(s) in the household trash.

Step 9: Wash teaspoon and the container with soap and warm water.

Step 10: Remove disposable gloves and throw them away in the household trash.

Step 11: Wash and dry your hands.

How should I store BOSULIF capsules?

- Store BOSULIF at room temperature between 68°F to 77°F (20°C to 25°C).
- Store the BOSULIF capsules in the original bottle.
- Ask your doctor or pharmacist about the right way to throw away outdated or unused BOSULIF.

Keep BOSULIF and all medicines out of the reach of children.

LAB-0639-13.0
For more information, go to www.Bosulif.com or www.pfizermedicalinformation.com or call 1-800-438-1985.
This Instructions for Use has been approved by the U.S. Food and Drug Administration.
Issued: 9 2023

PRINCIPAL DISPLAY PANEL - 100 mg Bottle Label

PROFESSIONAL SAMPLE – NOT FOR SALE

Pfizer
NDC 63539-117-01

Bosulif®
(bosutinib) tablets

100 mg*

Do not crush or cut tablet
For Oncology Use Only

120 Tablets
Rx only

PRINCIPAL DISPLAY PANEL - 400 mg Tablet Bottle Label

PROFESSIONAL SAMPLE – NOT FOR SALE

Pfizer
NDC 63539-193-30

Bosulif®
(bosutinib) tablets

400 mg*

Do not crush or cut tablet
For Oncology Use Only

30 Tablets
Rx only